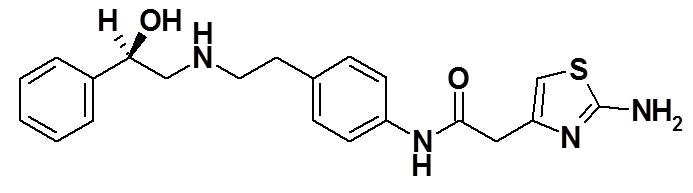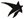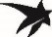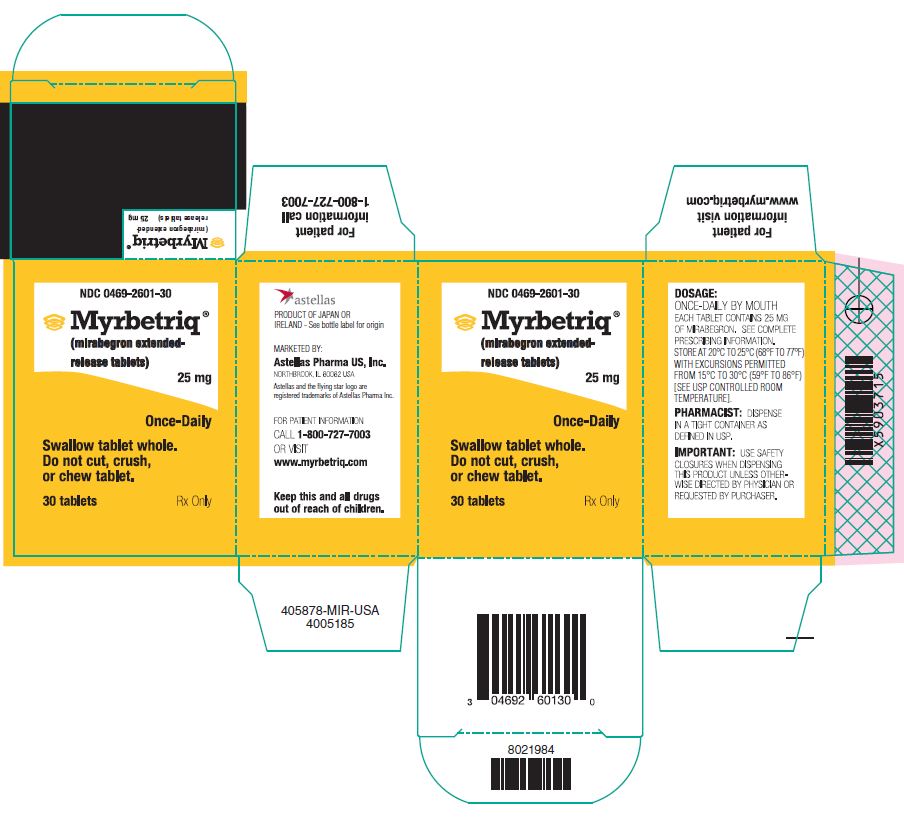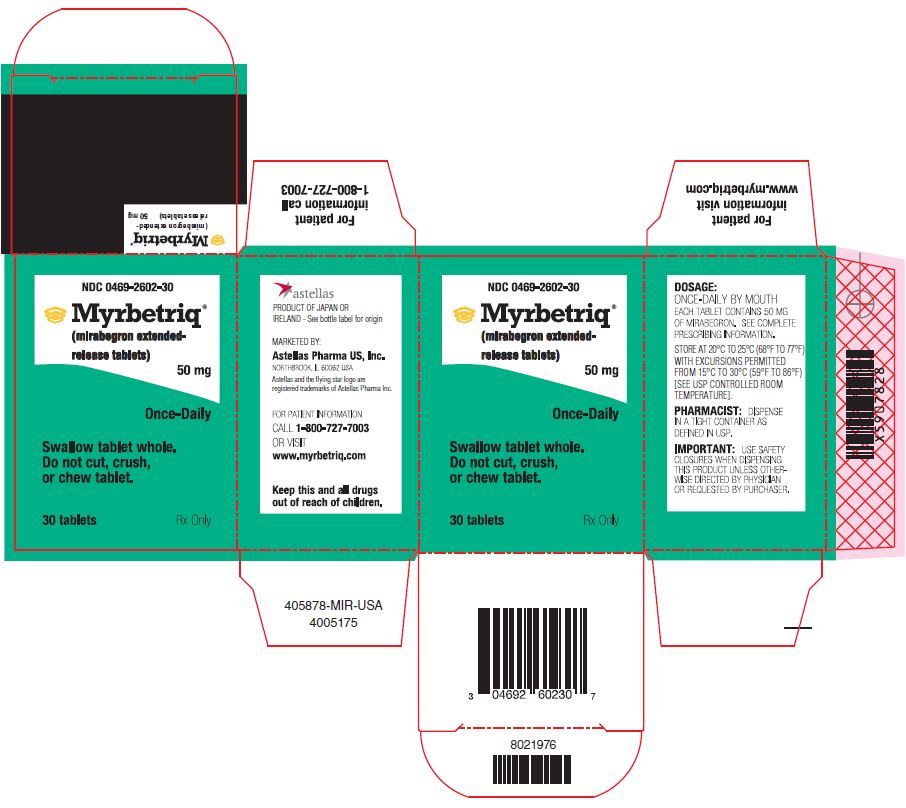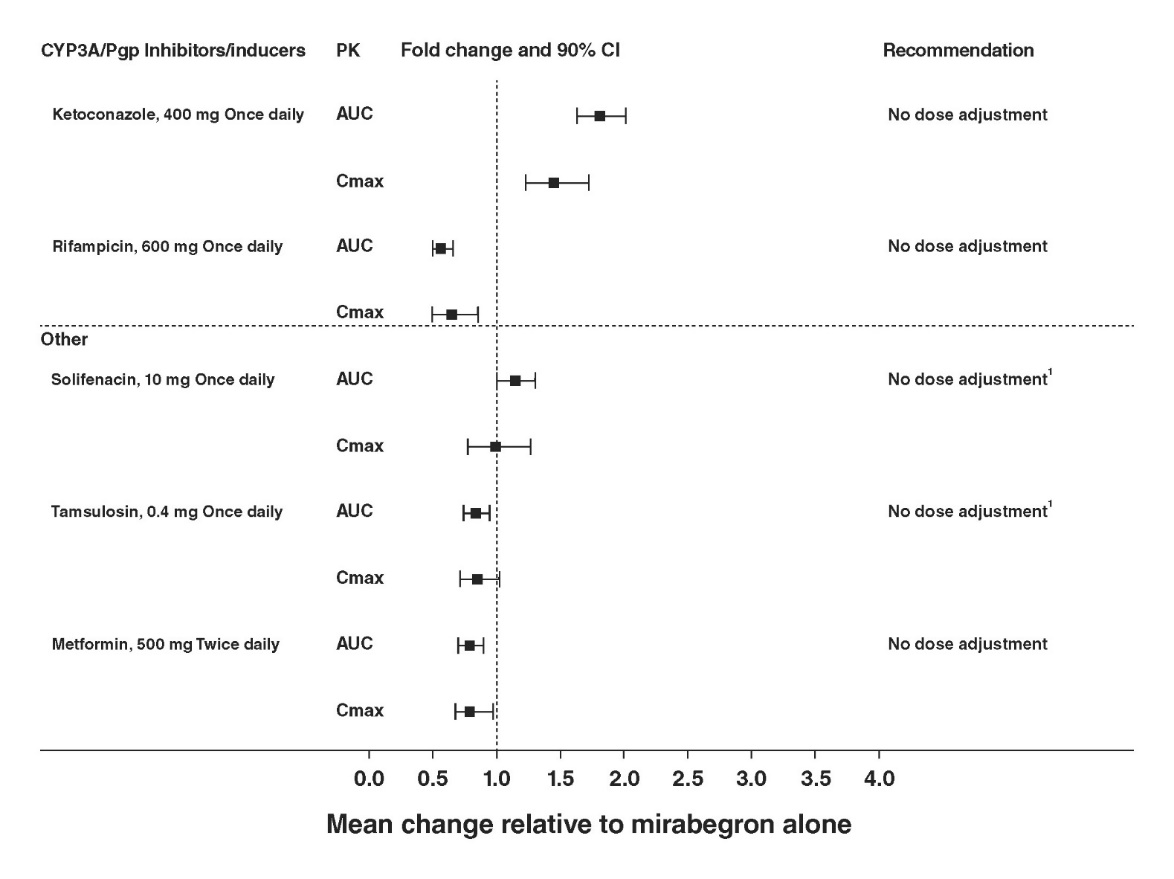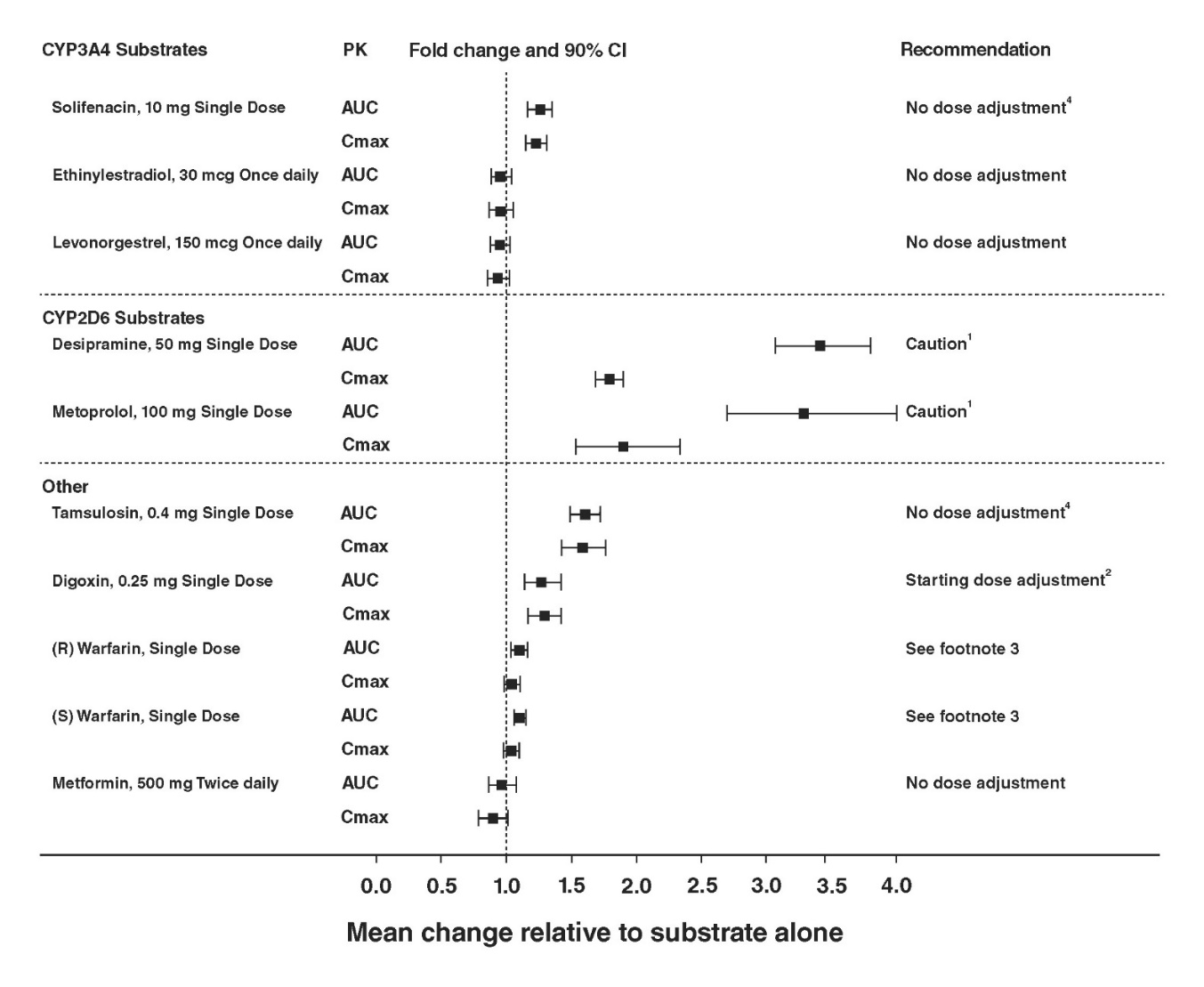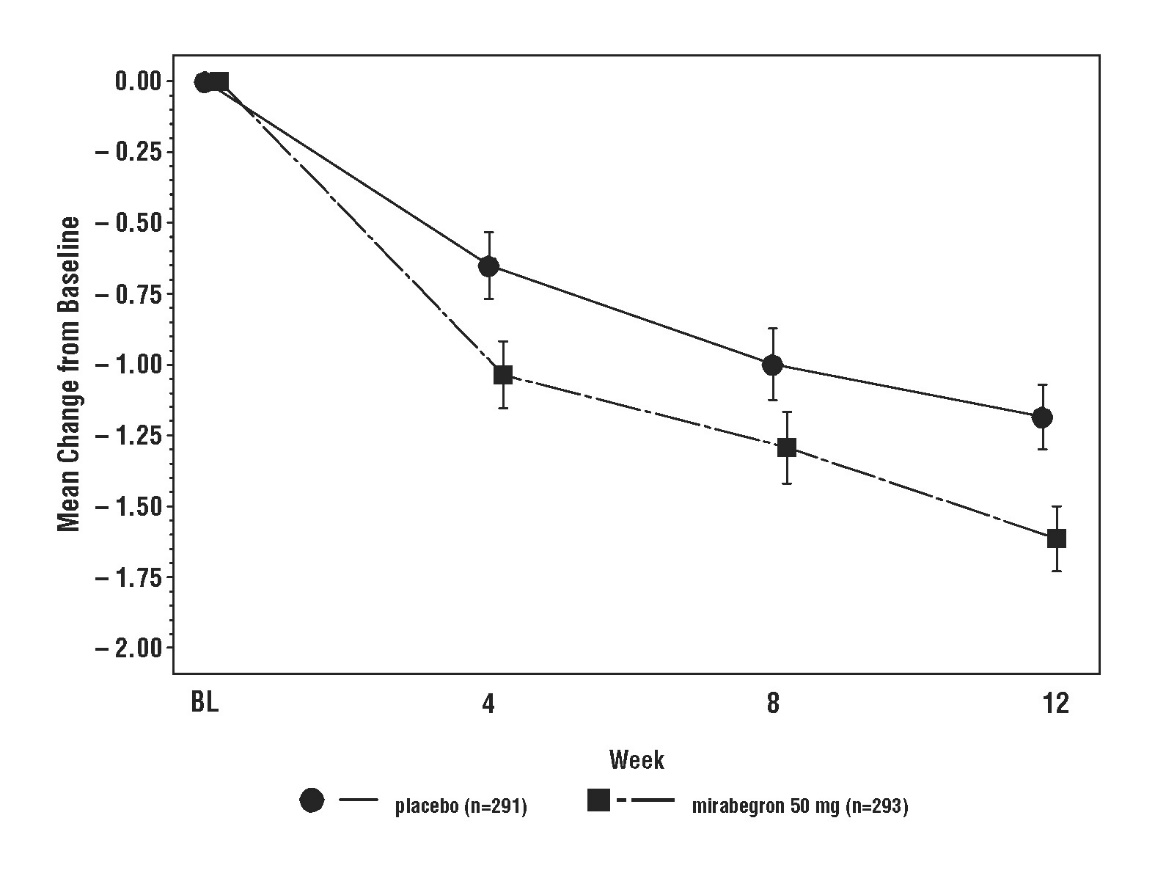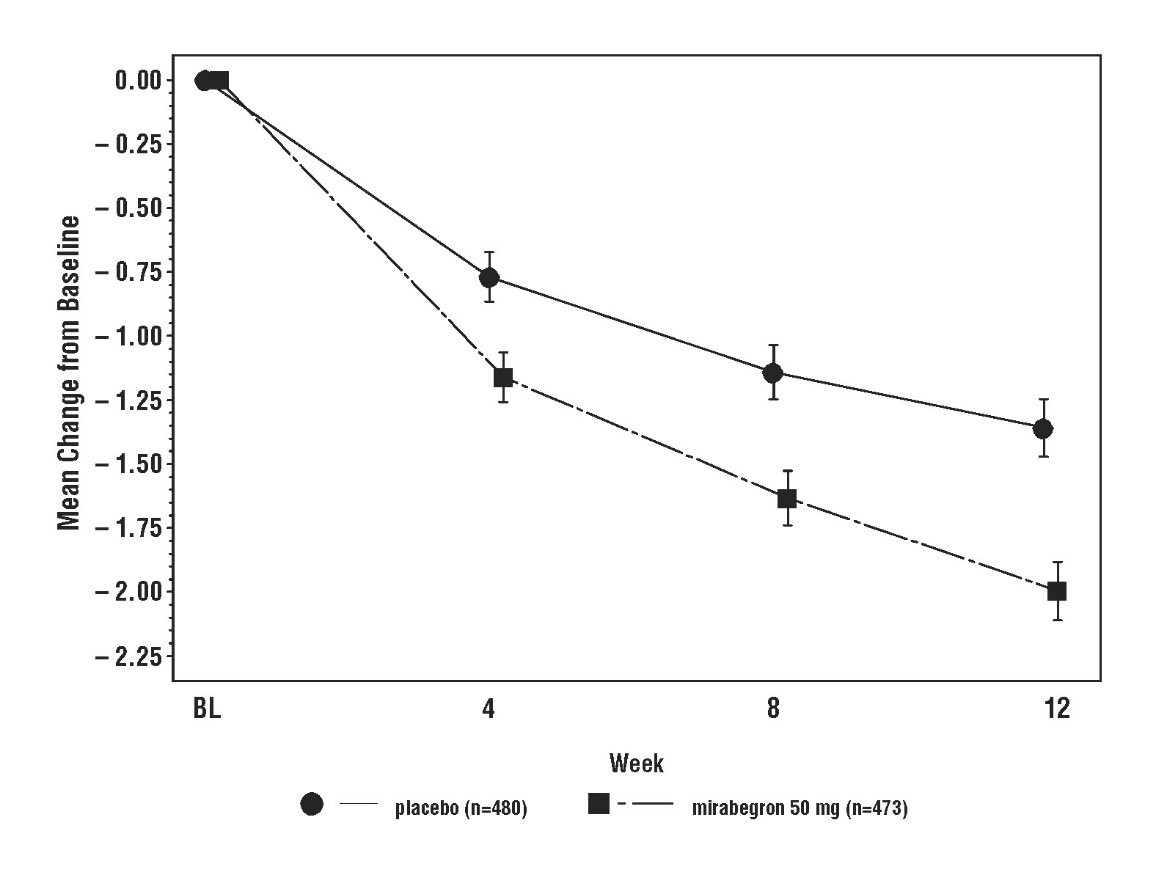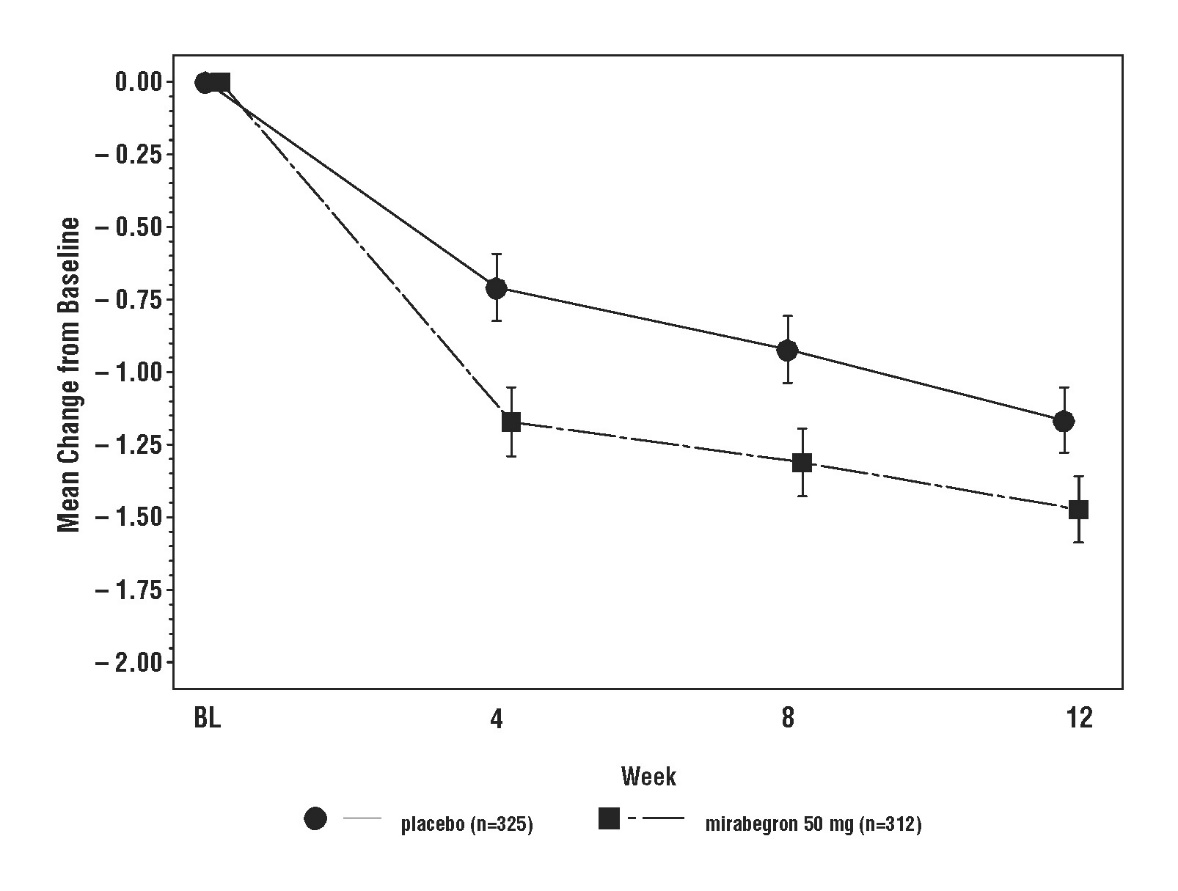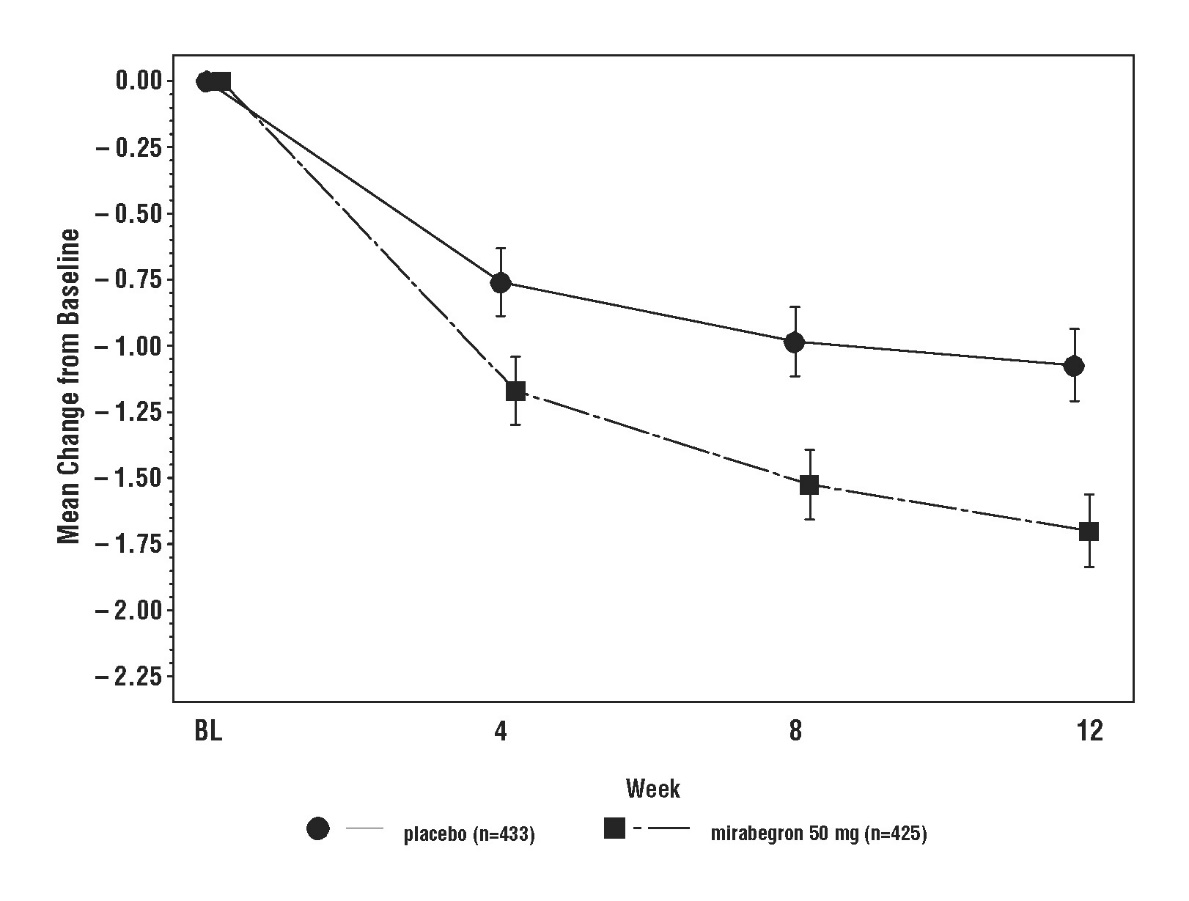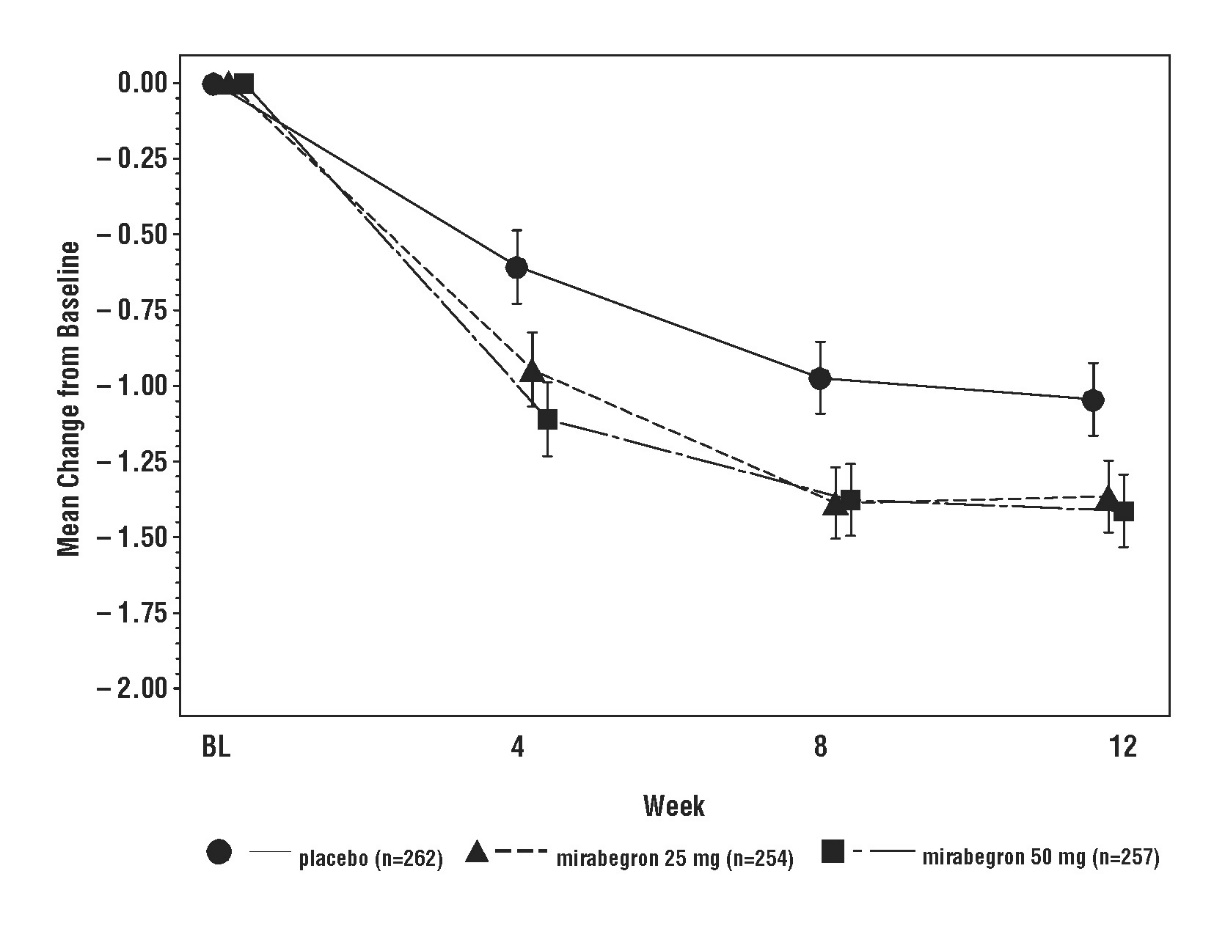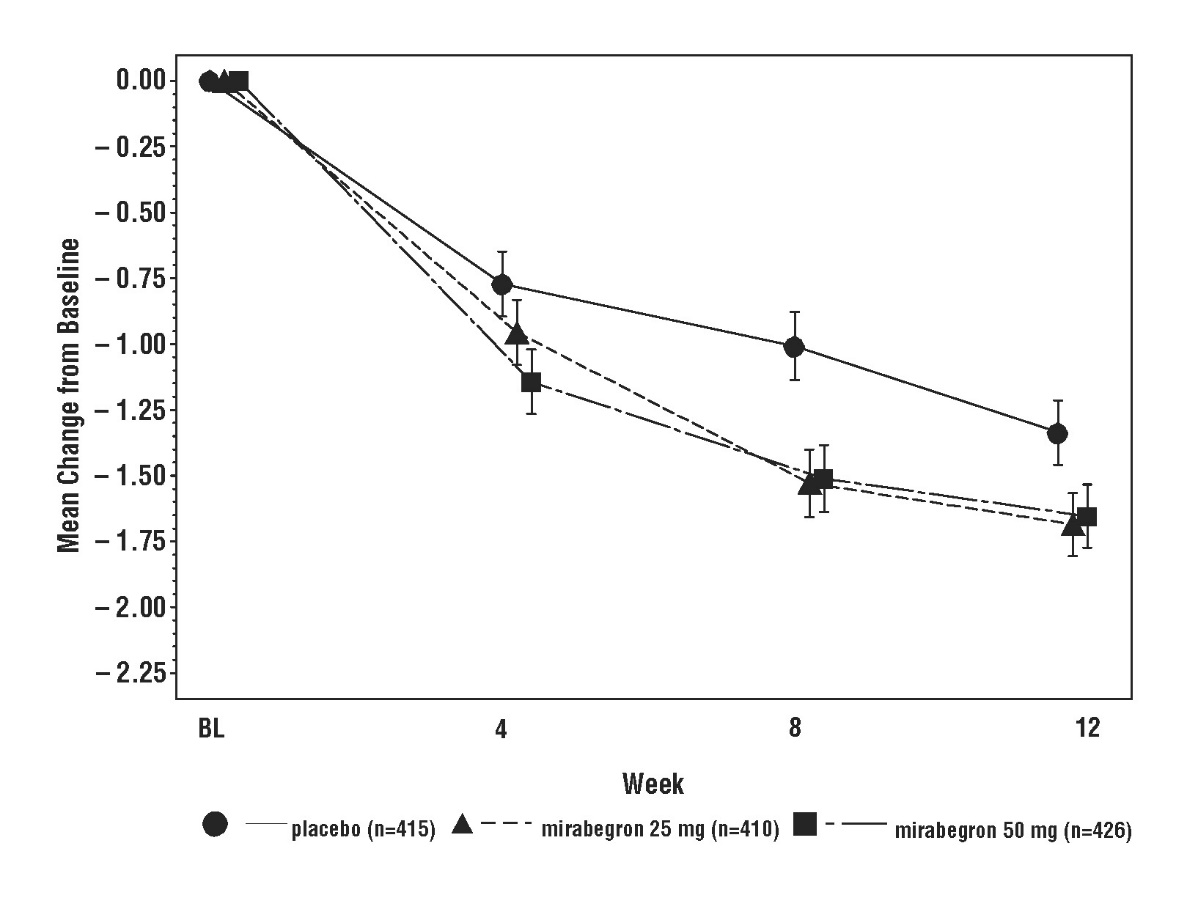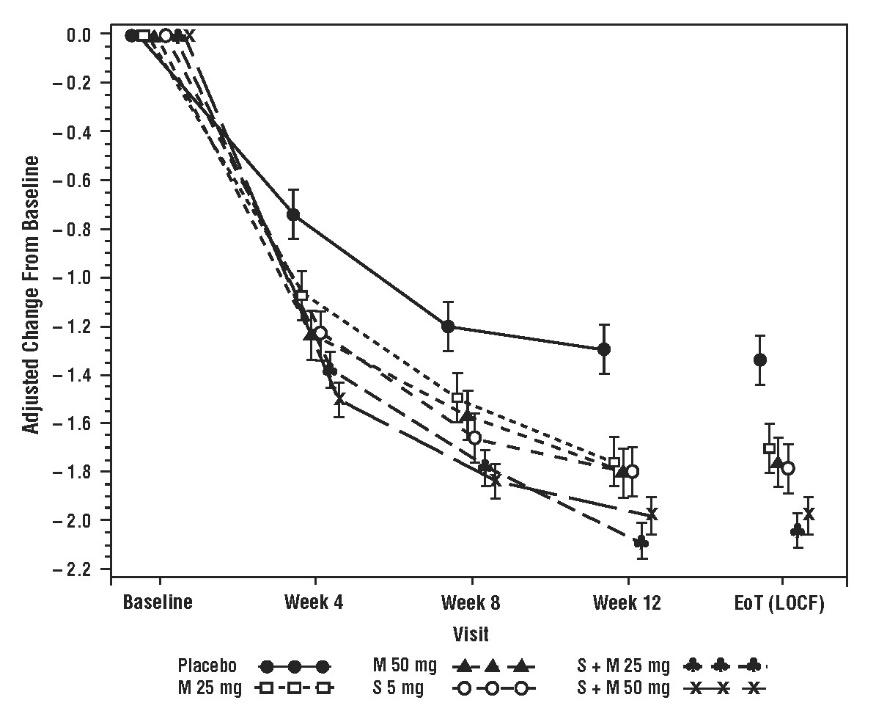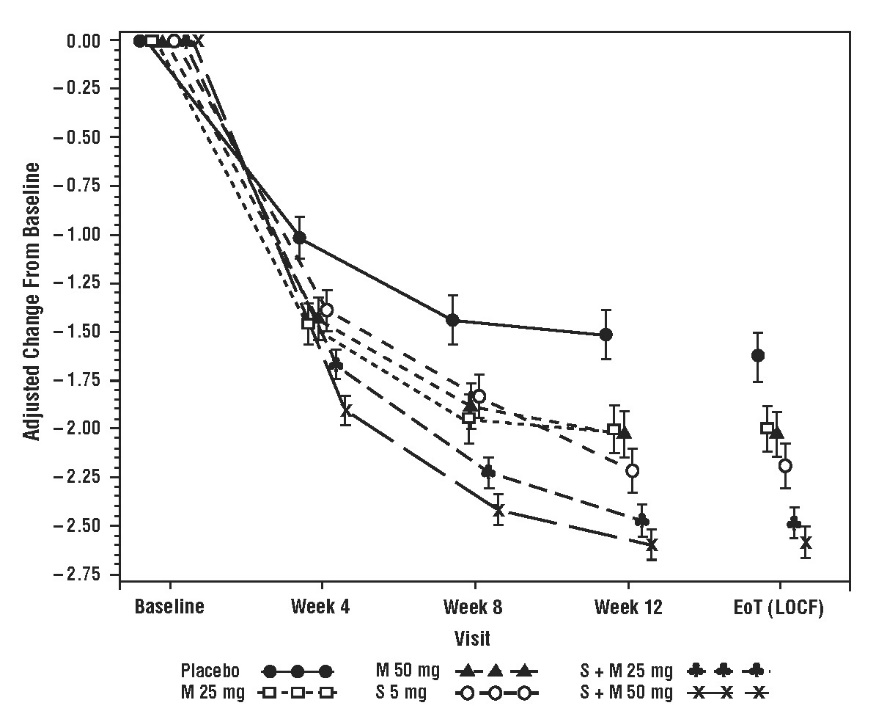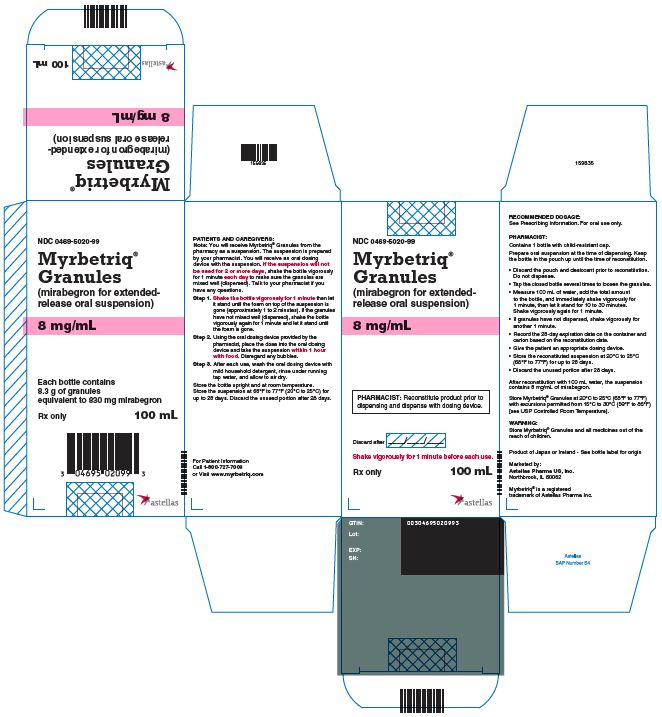 DRUG LABEL: Myrbetriq
NDC: 0469-2601 | Form: TABLET, FILM COATED, EXTENDED RELEASE
Manufacturer: Astellas Pharma US, Inc.
Category: prescription | Type: HUMAN PRESCRIPTION DRUG LABEL
Date: 20240801

ACTIVE INGREDIENTS: MIRABEGRON 25 mg/1 1
INACTIVE INGREDIENTS: POLYETHYLENE OXIDE 2000000; POLYETHYLENE GLYCOL 8000; HYDROXYPROPYL CELLULOSE (1600000 WAMW); BUTYLATED HYDROXYTOLUENE; MAGNESIUM STEARATE; HYPROMELLOSE 2910 (6 MPA.S); FERRIC OXIDE YELLOW; FERRIC OXIDE RED

HIGHLIGHTS OF PRESCRIBING INFORMATION

These highlights do not include all the information needed to use MYRBETRIQ®/MYRBETRIQ® GRANULES safely and effectively. See full prescribing information for MYRBETRIQ/MYRBETRIQ GRANULES.
MYRBETRIQ (mirabegron extended-release tablets), for oral use
MYRBETRIQ GRANULES (mirabegron for extended-release oral suspension)
Initial U.S. Approval: 2012

RECENT MAJOR CHANGES

Indications and Usage (1.2) 3/2021
Dosage and Administration (2) 3/2021

Warnings and Precautions, Increase in Blood Pressure (5.1) 3/2021

1 INDICATIONS AND USAGE

MYRBETRIQ is a beta-3 adrenergic agonist indicated for the treatment of:

- Overactive bladder (OAB) in adult patients with symptoms of urge urinary incontinence, urgency, and urinary frequency, either alone or in combination with the muscarinic antagonist solifenacin succinate. (1.1)
- Neurogenic detrusor overactivity (NDO) in pediatric patients aged 3 years and older and weighing 35 kg or more. (1.2)

MYRBETRIQ Granules is a beta-3 adrenergic agonist indicated for the treatment of NDO in pediatric patients aged 3 years and older. (1.2)

2 DOSAGE AND ADMINISTRATION

- MYRBETRIQ and MYRBETRIQ Granules are two different products and they are not substitutable on a milligram-per-milligram basis. Select the recommended product (MYRBETRIQ or MYRBETRIQ Granules) based on the indication and patient’s weight. Do not combine MYRBETRIQ and MYRBETRIQ Granules to achieve the total dose. A recommended dosage for MYRBETRIQ Granules for adults has not been determined. (2.1)
  OAB in Adults
- The recommended starting dose of MYRBETRIQ is 25 mg orally once daily, either alone or in combination with solifenacin succinate 5 mg orally once daily. (2.2)
- After 4 to 8 weeks, the MYRBETRIQ dose may be increased to 50 mg orally once daily. (2.2)
  NDO in Pediatric Patients 3 Years and Older
- Pediatric Patients weighing less than 35 kg: Use MYRBETRIQ Granules: The recommended starting dose of MYRBETRIQ Granules is weight-based and administered as an extended-release oral suspension once daily. After 4 to 8 weeks, increase to the lowest effective dose without exceeding the maximum recommended dose. (2.3)
- Pediatric Patients weighing 35 kg or more: Use MYRBETRIQ or MYRBETRIQ Granules:
  - The recommended starting dosage of MYRBETRIQ is 25 mg orally once daily. After 4 to 8 weeks, the MYRBETRIQ dose may be increased to 50 mg orally once daily. (2.3)
  - The recommended starting dosage of MYRBETRIQ Granules, administered as an extended-release oral suspension, is 6 mL (48 mg) orally once daily. After 4 to 8 weeks, increase to a maximum dosage of MYRBETRIQ Granules 10 mL (80 mg) orally once daily (2.3)

Adult or Pediatric Patients with Renal or Hepatic Impairment: Refer to the full prescribing information for recommended dosage. (2.4, 2.5)

Preparation for MYRBETRIQ Granules: Refer to the full prescribing information. (2.6)
Administration

- MYRBETRIQ:
  - Adult patients: Swallow MYRBETRIQ whole with water. Do not chew, divide, or crush. Take with or without food. (2.7)
  - Pediatric patients: Swallow MYRBETRIQ whole with water. Do not chew, divide, or crush. Take with food. (2.7)
- MYRBETRIQ Granules:
  - Pediatric patients: Take MYRBETRIQ Granules prepared as an extended-release oral suspension. Take with food. (2.7)

3 DOSAGE FORMS AND STRENGTHS

- Extended-release tablets: 25 mg and 50 mg (3)
- For extended-release oral suspension: 8 mg/mL of mirabegron after reconstitution (3)

4 CONTRAINDICATIONS

Hypersensitivity to mirabegron or any inactive ingredients. (4)

5 WARNINGS AND PRECAUTIONS

- Increases in Blood Pressure: Can increase blood pressure in adult or pediatric patients. Periodically monitor blood pressure, especially in hypertensive patients. MYRBETRIQ/MYRBETRIQ Granules are not recommended in patients with severe uncontrolled hypertension. (5.1)
- Urinary Retention in Patients With Bladder Outlet Obstruction and in Patients Taking Muscarinic Antagonist Drugs for Overactive Bladder: Administer with caution in these patients because of risk of urinary retention. (5.2)
- Angioedema: Angioedema of the face, lips, tongue, and/or larynx has been reported with mirabegron. (5.3, 6.2)

6 ADVERSE REACTIONS

- Most commonly reported adverse reactions with MYRBETRIQ monotherapy in adult patients with OAB (> 2% and > placebo) were hypertension, nasopharyngitis, urinary tract infection, and headache. (6.1)
- Most commonly reported adverse reactions with MYRBETRIQ, in combination with solifenacin succinate in adult patients with OAB (> 2% and > placebo and > comparator), were dry mouth, urinary tract infection, constipation, and tachycardia. (6.1)
- Most commonly reported adverse reactions with MYRBETRIQ/MYRBETRIQ Granules in pediatric patients with NDO (≥ 3%) were UTI, nasopharyngitis, constipation, and headache. (6.1)

To report SUSPECTED ADVERSE REACTIONS, contact Astellas Pharma US, Inc. at 1-800-727-7003 or FDA at 1-800-FDA-1088 or www.fda.gov/medwatch.

7 DRUG INTERACTIONS

- Drugs Metabolized by CYP2D6: Mirabegron is a CYP2D6 inhibitor and, when used concomitantly with drugs metabolized by CYP2D6, especially narrow therapeutic index drugs, appropriate monitoring and possible dose adjustment of those drugs may be necessary. (5.4, 7.1, 12.3)
- Digoxin: When initiating a combination of mirabegron and digoxin with or without solifenacin succinate, use the lowest dose of digoxin; monitor serum digoxin concentrations to titrate digoxin dose to desired clinical effect. (7.2, 12.3)

FULL PRESCRIBING INFORMATION

1 INDICATIONS AND USAGE

1.1 Adult Overactive Bladder (OAB)

MYRBETRIQ Monotherapy

MYRBETRIQ® is indicated for the treatment of OAB in adult patients with symptoms of urge urinary incontinence, urgency, and urinary frequency.

MYRBETRIQ Combination Therapy with Solifenacin Succinate

MYRBETRIQ, in combination with the muscarinic antagonist solifenacin succinate, is indicated for the treatment of OAB in adult patients with symptoms of urge urinary incontinence, urgency, and urinary frequency.

1.2 Pediatric Neurogenic Detrusor Overactivity (NDO)

MYRBETRIQ Granules

MYRBETRIQ® Granules is indicated for the treatment of NDO in pediatric patients aged 3 years and older.

MYRBETRIQ

MYRBETRIQ is indicated for the treatment of NDO in pediatric patients aged 3 years and older and weighing 35 kg or more.

2 DOSAGE AND ADMINISTRATION

2.1 Important Dosage Information

MYRBETRIQ and MYRBETRIQ Granules are two different products and they are not substitutable on a milligram-per-milligram basis:

• Select the recommended product (MYRBETRIQ or MYRBETRIQ Granules) based on the indication and patient’s weight [see Indications and Usage (1) and Dosage and Administration (2.2, 2.3, 2.4, 2.5)].
• Do not combine MYRBETRIQ and MYRBETRIQ Granules to achieve the total dose.
• A recommended dosage for MYRBETRIQ Granules for adults has not been determined.

2.2 Recommended Dosage for Adult Patients with OAB

MYRBETRIQ Monotherapy

The recommended starting dosage of MYRBETRIQ is 25 mg orally once daily. If needed, increase to the maximum dosage of MYRBETRIQ 50 mg orally once daily after 4 to 8 weeks. For administration instructions, see Dosage and Administration (2.7).

MYRBETRIQ Combination Therapy with Solifenacin Succinate

The recommended starting dosage for combination treatment is MYRBETRIQ 25 mg orally once daily and solifenacin succinate 5 mg orally once daily. If needed, increase to the maximum dosage of MYRBETRIQ 50 mg orally once daily after 4 to 8 weeks. Refer to the Prescribing Information for solifenacin succinate for additional information. For administration instructions, see Dosage and Administration (2.7).

2.3 Recommended Dosage for Pediatric Patients Aged 3 Years and Older with NDO

For pediatric patients 3 years of age and older, select the appropriate product (MYRBETRIQ or MYRBETRIQ Granules) based on the patient’s weight.

Pediatric Patients weighing less than 35 kg: Use MYRBETRIQ Granules

The recommended starting and maximum doses of MYRBETRIQ Granules, administered as extended-release oral suspension once daily [see Dosage and Administration (2.6)], are shown in Table 1. The recommended dosages are determined based on patient weight. Evaluate patients periodically for potential dosage adjustment. For administration instructions, see Dosage and Administration (2.7).

Table 1: MYRBETRIQ Granules Recommended Dosage for Pediatric Patients Aged 3 Years and Older Weighing Less Than 35 kg as an Extended-Release Oral Suspension (Administered Orally Once Daily)
Body Weight Range | Starting Dose | Maximum Volume
11 kg to less than 22 kg | 3 mL (24 mg) | 6 mL (48 mg)
22 kg to less than 35 kg | 4 mL (32 mg) | 8 mL (64 mg)
Greater than or equal to 35 kg | Refer to information in next section

Pediatric Patients weighing 35 kg or more: Use MYRBETRIQ or MYRBETRIQ Granules

The recommended starting dosage of MYRBETRIQ is 25 mg orally once daily. If needed, increase to a maximum dosage of MYRBETRIQ 50 mg orally once daily after 4 to 8 weeks. For administration instructions, see Dosage and Administration (2.7).

The recommended starting dosage of MYRBETRIQ Granules is 6 mL (48 mg) orally once daily. If needed, increase to a maximum dosage of MYRBETRIQ Granules 10 mL (80 mg) orally once daily after 4 to 8 weeks. For administration instructions, see Dosage and Administration (2.7).

2.4 Recommended Dosage in Adult Patients with Renal or Hepatic Impairment

Dosage in Adults with Renal Impairment

The recommended dosage of MYRBETRIQ (administered orally once daily) in adult patients with renal impairment is described in Table 2 [see Use in Specific Populations (8.6)]. For administration instructions, see Dosage and Administration (2.7).

Table 2: MYRBETRIQ Recommended Dosage in Adult Patients with Renal Impairment (Administered Orally Once Daily)
Estimated GFR [Estimated GFR using the modification of diet in renal disease (MDRD) formula] | Starting Dose | Maximum Dose
eGFR 30 to 89 mL/min/1.73 m^2 | 25 mg | 50 mg
eGFR 15 to 29 mL/min/1.73 m^2 | 25 mg | 25 mg
eGFR < 15 mL/min/1.73 m^2 or requiring dialysis | Not recommended

Dosage in Adults with Hepatic Impairment

The recommended dosage of MYRBETRIQ (administered orally once daily) in adult patients with hepatic impairment is described in Table 3 [see Use in Specific Populations (8.7)]. For administration instructions, see Dosage and Administration (2.7).

Table 3: MYRBETRIQ Recommended Dosage in Adult Patients with Hepatic Impairment (Administered Orally Once Daily)
Hepatic Impairment Classification | Starting Dose | Maximum Dose
Child-Pugh Class A (Mild hepatic impairment) | 25 mg | 50 mg
Child-Pugh Class B (Moderate hepatic impairment) | 25 mg | 25 mg
Child-Pugh Class C (Severe hepatic impairment) | Not Recommended

2.5 Recommended Dosage in Pediatric Patients with Renal or Hepatic Impairment

For pediatric patients 3 years of age and older, select the appropriate product (MYRBETRIQ or MYRBETRIQ Granules) based on the patient’s weight.

Pediatric Patients Weighing Less Than 35 kg with Renal or Hepatic Impairment: Use MYRBETRIQ Granules

Dosage in Pediatric Patients with Renal Impairment

The recommended dosage of MYRBETRIQ Granules in pediatric patients with renal impairment (administered orally once daily) is described in Table 4 [see Use in Specific Populations (8.6)]. For administration instructions, see Dosage and Administration (2.7).

Table 4: MYRBETRIQ Granules Recommended Dosage in Pediatric Patients Aged 3 Years and Older Weighing Less Than 35 kg with Renal Impairment (Administered Orally Once Daily)
Estimated GFR [Estimate GFR using a validated eGFR estimating equation for the pediatric age range of the approved indication.] | Body Weight Range | Starting Dose | Maximum Dose
eGFR 30 to 89 mL/min/1.73 m^2 | 11 kg to less than 22 kg | 3 mL (24 mg) | 6 mL (48 mg)
eGFR 30 to 89 mL/min/1.73 m^2 | 22 kg to less than 35 kg | 4 mL (32 mg) | 8 mL (64 mg)
eGFR 15 to 29 mL/min/1.73 m^2 | 11 kg to less than 22 kg | 3 mL (24 mg) | 3 mL (24 mg)
eGFR 15 to 29 mL/min/1.73 m^2 | 22 kg to less than 35 kg | 4 mL (32 mg) | 4 mL (32 mg)
eGFR < 15 mL/min/1.73 m^2 or undergoing dialysis | Use is Not Recommended

Dosage in Pediatric Patients with Hepatic Impairment

The recommended dosage of MYRBETRIQ Granules in pediatric patients with hepatic impairment (administered orally once daily) is described in Table 5 [see Use in Specific Populations (8.7)]. For administration instructions, see Dosage and Administration (2.7).

Table 5: MYRBETRIQ Granules Recommended Dosage in Pediatric Patients Aged 3 Years and Older Weighing Less Than 35 kg with Hepatic Impairment (Administered Orally Once Daily)
Hepatic Impairment Classification | Body Weight Range | Starting Dose | Maximum Dose
Child-Pugh Class A (Mild hepatic impairment) | 11 kg to less than 22 kg | 3 mL (24 mg) | 6 mL (48 mg)
Child-Pugh Class A (Mild hepatic impairment) | 22 kg to less than 35 kg | 4 mL (32 mg) | 8 mL (64 mg)
Child-Pugh Class B (Moderate hepatic impairment) | 11 kg to less than 22 kg | 3 mL (24 mg) | 3 mL (24 mg)
Child-Pugh Class B (Moderate hepatic impairment) | 22 kg to less than 35 kg | 4 mL (32 mg) | 4 mL (32 mg)
Child-Pugh Class C (Severe hepatic impairment) | Use is Not Recommended

Pediatric Patients weighing 35 kg or more with renal or hepatic impairment: Use MYRBETRIQ or MYRBETRIQ Granules

Dosage in Pediatric Patients with Renal Impairment

The recommended dosage of MYRBETRIQ in pediatric patients with renal impairment weighing 35 kg or more (administered orally once daily) is described in Table 2 (above). Note that the dosage is the same as for adult patients with renal impairment [see Dosage and Administration (2.4) and Use in Specific Populations (8.6)]. For administration instructions, see Dosage and Administration (2.7).

The recommended dosage of MYRBETRIQ Granules in pediatric patients with renal impairment weighing 35 kg or more (administered orally once daily) is described in Table 6 [see Use in Specific Populations (8.6)]. For administration instructions, see Dosage and Administration (2.7).

Table 6: MYRBETRIQ Granules Recommended Dosage in Pediatric Patients Aged 3 Years and Older with Renal Impairment Weighing 35 kg or More (Administered Orally Once Daily)
Estimated GFR [Estimate GFR using a validated eGFR estimating equation for the pediatric age range of the approved indication.] | Starting Dose | Maximum Dose
eGFR 30 to 89 mL/min/1.73 m^2 | 6 mL (48 mg) | 10 mL (80 mg)
eGFR 15 to 29 mL/min/1.73 m^2 | 6 mL (48 mg) | 6 mL (48 mg)
eGFR < 15 mL/min/1.73 m^2 or undergoing dialysis | Use is Not Recommended

Dosage in Pediatric Patients with Hepatic Impairment

The recommended dosage of MYRBETRIQ in pediatric patients with hepatic impairment weighing 35 kg or more (administered orally once daily) is described in Table 3 (above). Note that the dosage is the same as for adult patients with hepatic impairment [see Dosage and Administration (2.4) and Use in Specific Populations (8.6)]. For administration instructions, see Dosage and Administration (2.7).

The recommended dosage of MYRBETRIQ Granules in pediatric patients with hepatic impairment weighing 35 kg or more (administered orally once daily) is described in Table 7 [see Use in Specific Populations (8.7)]. For administration instructions, see Dosage and Administration (2.7).

Table 7: MYRBETRIQ Granules Recommended Dosage in Pediatric Patients Aged 3 Years and Older with Hepatic Impairment Weighing 35 kg or More (Administered Orally Once Daily)
Hepatic Impairment Classification | Starting Dose | Maximum Dose
Child-Pugh Class A (Mild hepatic impairment) | 6 mL (48 mg) | 10 mL (80 mg)
Child-Pugh Class B (Moderate hepatic impairment) | 6 mL (48 mg) | 6 mL (48 mg)
Child-Pugh Class C (Severe hepatic impairment) | Use is Not Recommended

2.6 Preparation and Storage Instructions for MYRBETRIQ Granules

The required dose for MYRBETRIQ Granules (mirabegron for extended-release oral suspension) is calculated based on the weight of the patient. Prepare oral suspension at the time of dispensing.

Keep the bottle in the pouch up until the time of reconstitution.

• Discard the pouch and desiccant prior to reconstitution. Do not dispense.
• Tap the closed bottle several times to loosen the granules.
• Measure 100 mL of water, add the total amount to the bottle, and immediately shake vigorously for 1 minute, then let it stand for 10 to 30 minutes. Shake vigorously again for 1 minute.
• If granules have not dispersed, shake vigorously for another 1 minute.
• Record the 28-day expiration date on the container and carton based on the reconstitution date.
• Give the patient an appropriate dosing device.
• Store the reconstituted suspension at 20°C to 25°C (68°F to 77°F) for up to 28 days.
• Discard the unused portion after 28 days [see How Supplied/Storage and Handling (16.2)].

After reconstitution with 100 mL water, the suspension contains 8 mg/mL of mirabegron.

2.7 Administration Instructions

Administration instructions for MYRBETRIQ and MYRBETRIQ Granules differ based on the patient population.

MYRBETRIQ

Adult patients: Swallow MYRBETRIQ whole with water. Do not chew, divide, or crush. Take with or without food.

Pediatric patients: Swallow MYRBETRIQ whole with water. Do not chew, divide, or crush. Take with food [see Use in Specific Populations (8.4)].

MYRBETRIQ Granules

Adult patients: A recommended dosage for MYRBETRIQ Granules for adults has not been determined.

Pediatric patients: Take MYRBETRIQ Granules prepared as an extended-release oral suspension [see Dosage and Administration (2.6)]. Take with food to reduce potential exposure-related risks [see Use in Specific Populations (8.4)].

2.8 Missed Dose

Instruct patients to take any missed doses as soon as they remember, unless more than 12 hours have passed since the missed dose. If more than 12 hours have passed, the missed dose can be skipped, and the next dose should be taken at the usual time.

3 DOSAGE FORMS AND STRENGTHS

MYRBETRIQ (mirabegron extended-release tablets) are supplied in two different strengths as described below:

• 25 mg oval, brown, film-coated tablet, debossed with the (Astellas logo) and “325”

• 50 mg oval, yellow, film-coated tablet, debossed with the (Astellas logo) and “355”

MYRBETRIQ Granules (mirabegron for extended-release oral suspension): Each bottle is filled with approximately 8.3 g of yellowish white granules, which contain 830 mg of mirabegron. After reconstitution with 100 mL water, the oral suspension is pale brownish yellow to yellow with 8 mg/mL of mirabegron.

4 CONTRAINDICATIONS

MYRBETRIQ/MYRBETRIQ Granules is contraindicated in patients with known hypersensitivity reactions to mirabegron or any inactive ingredients of the tablet or oral suspension [see Adverse Reactions (6.1, 6.2)].

5 WARNINGS AND PRECAUTIONS

5.1 Increases in Blood Pressure

Increases in Blood Pressure in Adults

MYRBETRIQ/MYRBETRIQ Granules can increase blood pressure. Periodic blood pressure determinations are recommended, especially in hypertensive patients. MYRBETRIQ/MYRBETRIQ Granules is not recommended for use in patients with severe uncontrolled hypertension (defined as systolic blood pressure greater than or equal to 180 mm Hg and/or diastolic blood pressure greater than or equal to 110 mm Hg) [see Clinical Pharmacology (12.2)].

In two, randomized, placebo-controlled, healthy adult volunteer studies, MYRBETRIQ was associated with dose-related increases in supine blood pressure. In these studies, at the maximum recommended dose of 50 mg, the mean maximum increase in systolic/diastolic blood pressure was approximately 3.5/1.5 mm Hg greater than placebo.

In contrast, in adult OAB patients in clinical trials, MYRBETRIQ, taken as monotherapy or in combination with solifenacin succinate 5 mg, the mean increase in systolic and diastolic blood pressure at the maximum recommended mirabegron dose of 50 mg was approximately 0.5 to 1 mm Hg greater than placebo. Worsening of pre-existing hypertension was reported infrequently in patients taking MYRBETRIQ.

Increases in Blood Pressure in Pediatric Patients 3 Years and Older

MYRBETRIQ/MYRBETRIQ Granules can increase blood pressure in pediatric patients. Blood pressure increases may be larger in children (3 to less than 12 years of age) than in adolescents (12 to less than 18 years of age). Periodic blood pressure determinations are recommended. MYRBETRIQ/MYRBETRIQ Granules is not recommended for use in pediatric patients with severe uncontrolled hypertension, defined as a systolic and/or diastolic blood pressure above the 99th percentile plus 5 mm Hg for age, sex, and stature using appropriate reference values [see Adverse Reactions (6.1)].

5.2 Urinary Retention in Patients with Bladder Outlet Obstruction and in Patients Taking Muscarinic Antagonist Medications for OAB

In patients taking MYRBETRIQ, urinary retention has been reported to occur in patients with bladder outlet obstruction (BOO) and in patients taking muscarinic antagonist medications for the treatment of OAB. A controlled clinical safety study in patients with BOO did not demonstrate increased urinary retention in patients treated with mirabegron; however, MYRBETRIQ should still be administered with caution to patients with clinically significant BOO. For example, monitor these patients for signs and symptoms of urinary retention. MYRBETRIQ should also be administered with caution to patients taking muscarinic antagonist medications for the treatment of OAB, including solifenacin succinate [see Clinical Pharmacology (12.2)].

5.3 Angioedema

Angioedema of the face, lips, tongue, and/or larynx has been reported with MYRBETRIQ/MYRBETRIQ Granules. In some cases, angioedema occurred after the first dose, however, cases have been reported to occur hours after the first dose or after multiple doses. Angioedema, associated with upper airway swelling, may be life-threatening. If involvement of the tongue, hypopharynx, or larynx occurs, promptly discontinue MYRBETRIQ/MYRBETRIQ Granules and provide appropriate therapy and/or measures necessary to ensure a patent airway [see Adverse Reactions (6.2)].

5.4 Patients Taking Drugs Metabolized by CYP2D6

Since MYRBETRIQ/MYRBETRIQ Granules is a moderate CYP2D6 inhibitor, the systemic exposure to CYP2D6 substrates is increased when coadministered with MYRBETRIQ/MYRBETRIQ Granules. Therefore, appropriate monitoring and dose adjustment may be necessary, especially with narrow therapeutic index drugs metabolized by CYP2D6 [see Drug Interactions (7.1) and Clinical Pharmacology (12.3)].

6 ADVERSE REACTIONS

The following adverse reactions are discussed in more detail in other sections of the labeling.

- Hypertension [see Warnings and Precautions (5.1)]
- Urinary Retention [see Warnings and Precautions (5.2)]
- Angioedema [see Warnings and Precautions (5.3)]

6.1 Clinical Trials Experience

Because clinical trials are conducted under widely varying conditions, adverse reaction rates observed in the clinical trials of a drug cannot be directly compared to rates in the clinical trials of another drug and may not reflect the rates observed in clinical practice.

MYRBETRIQ Monotherapy for Adult OAB

In three, 12-week, double-blind, placebo-controlled, safety and efficacy studies in patients with OAB (Studies 1, 2, and 3), MYRBETRIQ was evaluated for safety in 2736 patients [see Clinical Studies (14.1)]. Study 1 also included an active control. For the combined Studies 1, 2, and 3, 432 patients received MYRBETRIQ 25 mg, 1375 received MYRBETRIQ 50 mg, and 929 received MYRBETRIQ 100 mg once daily. In these studies, the majority of the patients were Caucasian (94%) and female (72%) with a mean age of 59 years (range 18 to 95 years).

MYRBETRIQ was also evaluated for safety in 1632 patients who received MYRBETRIQ 50 mg once daily (n=812 patients) or MYRBETRIQ 100 mg (n=820 patients) in a 1-year, randomized, fixed-dose, double-blind, active-controlled, safety study in patients with OAB (Study 4). Of these patients, 731 received MYRBETRIQ in a previous 12-week study. In Study 4, 1385 patients received MYRBETRIQ continuously for at least 6 months, 1311 patients received MYRBETRIQ for at least 9 months, and 564 patients received MYRBETRIQ for at least 1 year.

The most frequent adverse events (0.2%) leading to discontinuation in Studies 1, 2, and 3 for the 25 mg or 50 mg dose were nausea, headache, hypertension, diarrhea, constipation, dizziness, and tachycardia.

Atrial fibrillation (0.2%) and prostate cancer (0.1%) were reported as serious adverse events by more than 1 patient and at a rate greater than placebo.

Table 8 lists the adverse reactions, derived from all adverse events, that were reported in Studies 1, 2, and 3 at an incidence greater than placebo and in 1% or more of patients treated with MYRBETRIQ 25 mg or 50 mg once daily for up to 12 weeks. The most commonly reported adverse reactions (greater than 2% of MYRBETRIQ patients and greater than placebo) were hypertension, nasopharyngitis, urinary tract infection, and headache.

Table 8: Percentages of Patients with Adverse Reactions, Derived from All Adverse Events, Exceeding Placebo Rate and Reported in ≥ 1% of OAB Patients Treated with MYRBETRIQ 25 mg or 50 mg Once Daily in Studies 1, 2, and 3
Adverse Reaction | Placebo; (%) | MYRBETRIQ 25 mg; (%) | MYRBETRIQ 50 mg; (%)
Number of Patients | 1380 | 432 | 1375
Hypertension [Includes reports of blood pressure above the normal range, and BP increased from baseline, occurring predominantly in subjects with baseline hypertension.] | 7.6 | 11.3 | 7.5
Nasopharyngitis | 2.5 | 3.5 | 3.9
Urinary Tract Infection | 1.8 | 4.2 | 2.9
Headache | 3.0 | 2.1 | 3.2
Constipation | 1.4 | 1.6 | 1.6
Upper Respiratory Tract Infection | 1.7 | 2.1 | 1.5
Arthralgia | 1.1 | 1.6 | 1.3
Diarrhea | 1.3 | 1.2 | 1.5
Tachycardia | 0.6 | 1.6 | 1.2
Abdominal Pain | 0.7 | 1.4 | 0.6
Fatigue | 1.0 | 1.4 | 1.2

Other adverse reactions reported by less than 1% of patients treated with MYRBETRIQ in Studies 1, 2, or 3 included:

Cardiac disorders: palpitations, blood pressure increased [see Clinical Pharmacology (12.2)]
Eye disorders: glaucoma [see Clinical Pharmacology (12.2)]
Gastrointestinal disorders: dyspepsia, gastritis, abdominal distension
Infections and Infestations: sinusitis, rhinitis
Investigations: GGT increased, AST increased, ALT increased, LDH increased
Renal and urinary disorders: nephrolithiasis, bladder pain
Reproductive system and breast disorders: vulvovaginal pruritus, vaginal infection
Skin and subcutaneous tissue disorders: urticaria, leukocytoclastic vasculitis, rash, pruritus, purpura, lip edema

Table 9 lists the rates of the most commonly reported adverse reactions, derived from all adverse events in patients treated with MYRBETRIQ 50 mg for up to 52 weeks in Study 4. The most commonly reported adverse reactions (> 3% of MYRBETRIQ patients) were hypertension, urinary tract infection, headache, and nasopharyngitis.

Table 9: Percentages of Patients with Adverse Reactions, Derived from All Adverse Events, Reported in > 2% of OAB Patients Treated with MYRBETRIQ 50 mg Once Daily in Study 4
Adverse Reaction | MYRBETRIQ 50 mg; (%) | Active Control; (%)
Number of Patients | 812 | 812
Hypertension | 9.2 | 9.6
Urinary Tract Infection | 5.9 | 6.4
Headache | 4.1 | 2.5
Nasopharyngitis | 3.9 | 3.1
Back Pain | 2.8 | 1.6
Constipation | 2.8 | 2.7
Dry Mouth | 2.8 | 8.6
Dizziness | 2.7 | 2.6
Sinusitis | 2.7 | 1.5
Influenza | 2.6 | 3.4
Arthralgia | 2.1 | 2.0
Cystitis | 2.1 | 2.3

In Study 4, in patients treated with MYRBETRIQ 50 mg once daily, adverse reactions leading to discontinuation reported by more than 2 patients and at a rate greater than active control included: constipation (0.9%), headache (0.6%), dizziness (0.5%), hypertension (0.5%), dry eyes (0.4%), nausea (0.4%), vision blurred (0.4%), and urinary tract infection (0.4%). Serious adverse events reported by at least 2 patients and exceeding active control included cerebrovascular accident (0.4%) and osteoarthritis (0.2%). Serum ALT/AST increased from baseline by greater than 10-fold in 2 patients (0.3%) taking MYRBETRIQ 50 mg; and these markers subsequently returned to baseline while both patients continued MYRBETRIQ.

In Study 4, serious adverse events of neoplasm were reported by 0.1%, 1.3%, and 0.5% of patients treated with MYRBETRIQ 50 mg, MYRBETRIQ 100 mg, and active control once daily, respectively. Neoplasms reported by 2 patients treated with MYRBETRIQ 100 mg included breast cancer, lung neoplasm malignant, and prostate cancer. A causal relationship between mirabegron and these reported neoplasms has not been established.

In a separate clinical study in Japan, a single case was reported as Stevens-Johnson syndrome with increased serum ALT, AST, and bilirubin in a patient taking MYRBETRIQ 100 mg as well as an herbal medication (Kyufu Gold).

MYRBETRIQ Combination Therapy with Solifenacin Succinate for Adult OAB

In three, 12-week, double-blind, randomized, active-controlled safety and efficacy studies in patients with OAB (Studies 5, 6, and 7), combination treatment of MYRBETRIQ and solifenacin succinate was evaluated for safety in 6818 patients [see Clinical Studies (14.2)]. Studies 5 and 6 also included a placebo control. For the combined Studies 5, 6, and 7, 997 patients received combination treatment with MYRBETRIQ 25 mg and solifenacin succinate 5 mg, and 1706 patients received combination treatment with MYRBETRIQ 50 mg and solifenacin succinate 5 mg. In these studies, the majority of the patients were Caucasian (88%) and female (77%) with a mean age of 57 years (range 18 to 89 years).

MYRBETRIQ 50 mg and solifenacin succinate 5 mg coadministration was also evaluated for safety in 1814 patients in a 52-week, double-blind, randomized, active-controlled study in patients with OAB (Study 8) [see Clinical Studies (14.2)].

In Studies 5, 6, and 7, the most commonly reported adverse reactions (greater than 2% of patients treated with combination therapy of MYRBETRIQ and solifenacin succinate 5 mg, and greater than placebo and/or MYRBETRIQ or solifenacin succinate comparator at the same dose as in the combination treatment) were dry mouth, urinary tract infection, constipation, and tachycardia. The most frequent adverse reactions (≥ 0.2%) leading to discontinuation in the coadministration trials were dry mouth and urinary retention.

Table 10 lists the adverse reactions, derived from all adverse events that were reported in Studies 5, 6, and 7 in 1% or more of patients treated with MYRBETRIQ 25 mg or 50 mg coadministered with solifenacin succinate 5 mg and at an incidence greater than placebo and mirabegron or solifenacin succinate comparator at the same dose as in the combination treatment when administered once daily for up to 12 weeks.

Table 10: Percentages of Patients with Adverse Reactions, Derived from All Adverse Events, Exceeding Placebo and Comparator (at same dose level) Rate and Reported in ≥ 1% of OAB Patients Treated with Combination Therapy in Studies 5, 6, and 7 [Adverse reactions occurring in patients treated with coadministration of MYRBETRIQ and solifenacin succinate in Study 7, that included a 4-week initial treatment period with MYRBETRIQ 25 mg + Solifenacin Succinate 5 mg, are included in the MYRBETRIQ 50 mg + Solifenacin Succinate 5 mg group.]
Adverse; Reaction | Placebo; (%) | MYRBETRIQ; 25 mg; (%) | MYRBETRIQ; 50 mg; (%) | Solifenacin Succinate; 5 mg; (%) | MYRBETRIQ; 25 mg + Solifenacin Succinate; 5 mg; (%) | MYRBETRIQ; 50 mg + Solifenacin Succinate; 5 mg; (%)
Number of Patients | 510 | 500 | 500 | 1288 | 997 | 1706
Dry Mouth | 2.2 | 3.8 | 3.6 | 6.5 | 9.3 | 7.2
Urinary Tract Infections [Includes any recorded treatment-emergent UTI.] | 5.3 | 4.0 | 4.2 | 3.6 | 7.0 | 4.0
Constipation | 1.2 | 1.2 | 2.8 | 2.4 | 4.2 | 3.9
Tachycardia | 0.8 | 1.6 | 1.6 | 0.7 | 2.2 | 0.9
Dyspepsia | 0.6 | 0.4 | 0.2 | 0.7 | 1.1 | 1.3
Dizziness | 0.4 | 0.8 | 1.2 | 1.2 | 1.3 | 0.4
Vision Blurred | 0.4 | 0.2 | 0.2 | 0.9 | 0.7 | 1.1
Arthralgia | 0.8 | 0.8 | 0.8 | 0.8 | 0.5 | 1.1

In Study 8, the most common adverse reactions (more than 2% of patients treated with coadministration of MYRBETRIQ and solifenacin succinate and exceeding comparator rate) were UTI, dry mouth, constipation, and headache. The most frequent adverse reactions leading to discontinuation in the trial were constipation (0.2%), urinary retention (0.2%), urinary hesitation (0.2%), and vision blurred (0.2%).

In Study 8, serious adverse events of neoplasm were reported by 0.7%, 0.3%, and 0% of patients who received coadministration of MYRBETRIQ 50 mg and solifenacin succinate 5 mg, MYRBETRIQ 50 mg monotherapy, and solifenacin succinate 5 mg monotherapy, respectively. Neoplasms reported by more than 1 patient who received coadministration with MYRBETRIQ 50 mg and solifenacin succinate 5 mg included basal cell carcinoma (n=3), breast cancer (n=2), melanoma (n=2), and squamous cell carcinoma (n=2). A causal relationship between the coadministration of mirabegron and solifenacin succinate and these reported neoplasms has not been established.

Table 11 lists the adverse reactions, derived from all adverse events that were reported at an incidence greater than comparator and in 2% or more of patients treated with MYRBETRIQ 50 mg coadministered with solifenacin succinate 5 mg once daily for up to 52 weeks in Study 8.

Table 11: Percentages of Patients with Adverse Reactions, Derived from All Adverse Events, Exceeding Comparator Rate and Reported in ≥ 2% of OAB Patients Treated with Combination Therapy in Study 8
Adverse Reaction | MYRBETRIQ; 50 mg; (%) | Solifenacin Succinate; 5 mg; (%) | MYRBETRIQ; 50 mg + Solifenacin Succinate; 5 mg; (%)
Number of Patients | 305 | 303 | 1206
Urinary Tract Infections [Includes any recorded treatment-emergent UTI.] | 6.2 | 5.9 | 8.4
Dry Mouth | 3.9 | 5.9 | 6.1
Constipation | 1.0 | 2.3 | 3.3
Headache | 1.6 | 1.7 | 2.9

MYRBETRIQ/MYRBETRIQ Granules for Pediatric Neurogenic Detrusor Overactivity (NDO)

The safety of MYRBETRIQ/MYRBETRIQ Granules was evaluated in a 52-week, open-label, baseline-controlled, multicenter, dose titration study (Study 9) [see Clinical Studies (14.3)]. The study included 86 pediatric patients 3 to 17 years of age with neurogenic detrusor overactivity (NDO); 55% were female, 72% were White. Treatment was initiated at the weight-based starting recommended dose and was increased to a dose equivalent of MYRBETRIQ 50 mg daily dose in adults by Week 8. Subsequent to the dose titration period, patients continued their optimized dose for the duration of the 52-week study (mean exposure duration 303 days, range 1 to 390 days).

The most commonly reported adverse reactions were UTI, nasopharyngitis, constipation, and headache.

Table 12 lists the adverse reactions that were reported in 2% or more of patients treated with MYRBETRIQ/MYRBETRIQ Granules for oral suspension in Study 9.

Table 12: Percentages of Patients with Adverse Reactions Reported in ≥ 2% of Patients 3 to 17 Years of Age with Neurogenic Detrusor Overactivity (NDO) Treated with MYRBETRIQ/MYRBETRIQ Granules in Study 9
Adverse Reaction | Percentage (%) of Patients Reporting; Adverse Reactions; N=86
Number of Patients | 51 (59.3)
Urinary Tract Infection [Includes any recorded UTI while patient was on treatment with MYRBETRIQ/MYRBETRIQ Granules.] | 24.4
Nasopharyngitis | 5.8
Constipation | 4.7
Headache | 3.5
Nausea | 2.3
Gastroenteritis | 2.3
Rhinitis | 2.3
Cough | 2.3

Increased Blood Pressure in Pediatric Patients with NDO Treated with MYRBETRIQ/MYRBETRIQ Granules:

Mean systolic and diastolic blood pressures increased in Study 9 by 4.3 mm Hg and 1.7 mm Hg, respectively, in patients less than 12 years of age on MYRBETRIQ/MYRBETRIQ Granules at a dose equivalent of MYRBETRIQ 50 mg daily dose in adults. The blood pressure increases were larger in patients less than 8 years of age with mean systolic and diastolic blood pressure increases of 5.9 mm Hg and 2.3 mm Hg, respectively. Ten (24%) patients less than 12 years of age who were normotensive at baseline had at least one blood pressure measured at or above the 95th percentile for age, sex, and stature during Study 9. Stage 1 hypertension, defined as repeated blood pressure measurements at or above the 95th percentile for age, sex, and stature, was sustained in six of these 10 patients (60%) at the end of the study.

6.2 Postmarketing Experience

The following adverse reactions have been identified during post-approval use of MYRBETRIQ/MYRBETRIQ Granules. Because these reactions are reported voluntarily from a population of uncertain size, it is not always possible to reliably estimate their frequency or establish a causal relationship to drug exposure. The following events have been reported in association with mirabegron use in worldwide postmarketing experience:

Cardiac disorders: atrial fibrillation
Gastrointestinal disorders: nausea, constipation, diarrhea
Nervous system disorders: dizziness, headache

There have been postmarketing reports of confusion, hallucinations, insomnia, and anxiety in patients taking mirabegron. The majority of these patients had pre-existing medical conditions or concomitant medications that may cause confusion, hallucinations, insomnia, and anxiety. A causal relationship between mirabegron and these disorders has not been established.

Skin and subcutaneous tissue disorders: angioedema of the face, lips, tongue, and larynx, with or without respiratory symptoms [see Warnings and Precautions (5.3)]; pruritus
Renal and urinary disorders: urinary retention [see Warnings and Precautions (5.2)]

7 DRUG INTERACTIONS

Drug interaction studies were conducted in adult patients to investigate the effect of coadministered drugs on the pharmacokinetics of mirabegron and the effect of mirabegron on the pharmacokinetics of coadministered drugs (e.g., ketoconazole, rifampin, solifenacin succinate, tamsulosin, and oral contraceptives) [see Clinical Pharmacology (12.3)]. No dose adjustment is recommended when these drugs are coadministered with mirabegron.

The following are drug interactions for which monitoring is recommended:

7.1 Drugs Metabolized by CYP2D6

Since mirabegron is a moderate CYP2D6 inhibitor, the systemic exposure of drugs metabolized by CYP2D6 enzyme is increased when coadministered with mirabegron. Therefore, appropriate monitoring and dose adjustment may be necessary when MYRBETRIQ/MYRBETRIQ Granules is coadministered with these drugs, especially with narrow therapeutic index CYP2D6 substrates [see Warnings and Precautions (5.4) and Clinical Pharmacology (12.3)].

7.2 Digoxin

When given in combination, 100 mg mirabegron increased mean digoxin Cmax from 1.01 to 1.3 ng/mL (29%) and AUC from 16.7 to 19.3 ng.h/mL (27%). Concomitant administration of 0.25 mg digoxin with a combination of 5 mg solifenacin and 50 mg mirabegron increased digoxin AUCtau and Cmax by approximately 10% and 14%, respectively. For patients who are initiating a combination of mirabegron and digoxin, the lowest dose for digoxin should initially be considered. Serum digoxin concentrations should be monitored and used for titration of the digoxin dose to obtain the desired clinical effect [see Clinical Pharmacology (12.3)].

7.3 Warfarin

The mean Cmax of S- and R-warfarin was increased by approximately 4% and AUC by approximately 9% when administered as a single dose of 25 mg after multiple doses of 100 mg mirabegron. Following a single dose administration of 25 mg warfarin, mirabegron had no effect on the warfarin pharmacodynamic endpoints such as International Normalized Ratio (INR) and prothrombin time. However, the effect of mirabegron on multiple doses of warfarin and on warfarin pharmacodynamic end points such as INR and prothrombin time has not been fully investigated [see Clinical Pharmacology (12.3)].

8 USE IN SPECIFIC POPULATIONS

8.1 Pregnancy

Risk Summary

There are no studies with the use of MYRBETRIQ/MYRBETRIQ Granules in pregnant women or adolescents to inform a drug-associated risk of major birth defects, miscarriages, or adverse maternal or fetal outcomes. Mirabegron administration to pregnant animals during organogenesis resulted in reversible skeletal variations (in rats) at 22-fold (via AUC) the maximum recommended human dose (MRHD) of 50 mg/day and decreased fetal body weights (in rabbits) at 14-fold the MRHD. At maternally-toxic exposures in rats (96-fold), decreased fetal weight and increased fetal mortality were observed and, in rabbits (36-fold), cardiac findings (fetal cardiomegaly and fetal dilated aortae) were observed [see Data].

The estimated background risks of major birth defects and miscarriage for the indicated populations are unknown. In the U.S. general population, the estimated background risk of major birth defects or miscarriage in clinically recognized pregnancies are 2-4% and 15-20%, respectively.

Data

Animal Data

No embryo-fetal lethality or morphological fetal developmental abnormalities were produced in pregnant rats following daily oral administration of mirabegron during the period of organogenesis (Days 7 to 17 of gestation) at 0, 10, 30, 100, or 300 mg/kg, doses which were associated with systemic exposures (AUC) 0, 1, 6, 22, and 96-fold the MRHD. Skeletal variations (wavy ribs, delayed ossification) were observed in fetuses at doses 22-fold the systemic exposure at the MRHD and were reversible during development. Exposures 96-fold the MRHD were maternally-toxic (mortality, decreased body weight gain) and associated with fetal growth reduction.

Pregnant rabbits were treated with daily oral doses of mirabegron at 0, 3, 10, or 30 mg/kg/day during the period of organogenesis (Days 6 to 20 of gestation), which resulted in plasma exposures that were 0, 1, 14, or 36-fold the MRHD based on AUC. At 10 mg/kg/day (14-fold the MRHD) and higher, fetal body weights were reduced. At 30 mg/kg/day, maternal toxicity (increased heart rate, mortality, reduced body weight gain, reduced food consumption) occurred, and fetal deaths, fetal cardiomegaly and fetal dilated aortae were observed at systemic exposure levels (AUC) 36-fold the MRHD.

In a pre- and postnatal developmental study, rats were treated with daily oral doses of mirabegron at 0, 10, 30, or 100 mg/kg/day (0, 1, 6, or 22-fold the MRHD) from day 7 of gestation until day 20 after birth. Decreased maternal body weight was observed along with decreased pup survival in the first few days after birth (92.7% survival) compared to the control group (98.8% survival), at 100 mg/kg/day (22-fold the MRHD). Pup body weight gain was reduced until postnatal day 7 but not further affected throughout the remainder of the lactation period. In utero and lactational exposure did not affect developmental milestones, behavior, or fertility of offspring. No effects were observed at 30 mg/kg/day.

8.2 Lactation

Risk Summary

There are no data on the presence of mirabegron in human milk, the effects on the breastfed child, or the effects on milk production. Mirabegron-related material was present in rat milk and in the stomach of nursing pups following administrations of a single 10 mg/kg oral dose of ^14C-labeled mirabegron to lactating rats. When a drug is present in animal milk, it is likely that the drug will be present in human milk.

The developmental and health benefits of breastfeeding should be considered along with the mother’s clinical need for MYRBETRIQ/MYRBETRIQ Granules and any potential adverse effects on the breastfed child from mirabegron or from the underlying maternal condition.

8.4 Pediatric Use

The safety and effectiveness have been established only for the following pediatric indications:

- MYRBETRIQ: Treatment of neurogenic detrusor overactivity (NDO) in pediatric patients 3 years of age and older and weighing 35 kg or more.
- MYRBETRIQ Granules: Treatment of neurogenic detrusor overactivity (NDO) in pediatric patients 3 years of age and older.

The safety and effectiveness of MYRBETRIQ/MYRBETRIQ Granules in pediatric patients aged 3 years and older have been established for the treatment of neurogenic detrusor overactivity (NDO) and the information on this use is discussed throughout the labeling. Use of MYRBETRIQ/MYRBETRIQ Granules for this indication is supported by evidence from a 52-week, open-label, baseline-controlled, multicenter, dose titration trial in pediatric patients 3 years of age and older with NDO (Study 9) [see Adverse Reactions (6.1), Clinical Studies (14.3)]. Results showed an improvement from baseline in maximum cystometric (bladder) capacity (MCC) with MYRBETRIQ/MYRBETRIQ Granules use [see Clinical Studies (14.3)]. The most commonly reported adverse reactions in Study 9 (≥ 3%) were UTI, nasopharyngitis, constipation, and headache. Increased mean systolic and diastolic blood pressures with use of MYRBETRIQ/MYRBETRIQ Granules occurred in patients less than 12 years of age with larger increases in patients younger than 8 years of age [see Adverse Reactions (6.1)].
Take MYRBETRIQ/MYRBETRIQ Granules with food to reduce potential exposure-related risks, such as increased heart rate, as predicted by modeling of vital signs data in Study 9 [see Clinical Pharmacology (12.3)].

8.5 Geriatric Use

Of 5648 patients who received MYRBETRIQ monotherapy in the phase 2 and 3 studies for OAB, 2029 (35.9%) were 65 years of age or older, and 557 (9.9%) were 75 years of age or older. No overall differences in safety or effectiveness were observed between patients younger than 65 years of age and those 65 years of age or older in these studies.

8.6 Renal Impairment

MYRBETRIQ/MYRBETRIQ Granules have not been studied in patients with End-Stage Renal Disease (eGFR < 15 mL/min/1.73 m^2) or patients requiring hemodialysis and, therefore, is not recommended for use in these patient populations. No dose adjustment is necessary in patients with mild or moderate renal impairment (eGFR 30 to 89 mL/min/1.73 m^2).

In adult patients with severe renal impairment (eGFR 15 to 29 mL/min/1.73 m^2), the daily dose of MYRBETRIQ should not exceed 25 mg. In pediatric patients with severe renal impairment, the daily dose of MYRBETRIQ/MYRBETRIQ Granules should not exceed the recommended starting dose [see Clinical Pharmacology (12.3)].

8.7 Hepatic Impairment

MYRBETRIQ/MYRBETRIQ Granules have not been studied in patients with severe hepatic impairment (Child-Pugh Class C) and, therefore, is not recommended for use in this patient population. No dose adjustment is necessary in patients with mild hepatic impairment (Child-Pugh Class A).

In adult patients with moderate hepatic impairment (Child-Pugh Class B), the daily dose of MYRBETRIQ should not exceed 25 mg. In pediatric patients with moderate hepatic impairment (Child-Pugh Class B), the daily dose of MYRBETRIQ/MYRBETRIQ Granules should not exceed the recommended starting dose [see Clinical Pharmacology (12.3)].

10 OVERDOSAGE

Mirabegron has been administered to healthy volunteers at single doses up to 400 mg. At this dose, adverse events reported included palpitations (1 of 6 subjects) and increased pulse rate exceeding 100 beats per minute (bpm) (3 of 6 subjects). Multiple doses of mirabegron up to 300 mg daily for 10 days showed increases in pulse rate and systolic blood pressure when administered to healthy volunteers. Treatment for overdosage should be symptomatic and supportive. In the event of overdosage, pulse rate, blood pressure and ECG monitoring is recommended.

11 DESCRIPTION

MYRBETRIQ (mirabegron extended-release tablets) for oral use and MYRBETRIQ Granules (mirabegron for extended-release oral suspension) are beta-3 adrenergic agonists.

The chemical name of mirabegron is 2-(2-aminothiazol-4-yl)-N-[4-(2-{[(2R)-2-hydroxy-2-phenylethyl]amino}ethyl)phenyl]acetamide having an empirical formula of C21H24N4O2S and a molecular weight of 396.51. The structural formula of mirabegron is:

Mirabegron is a white powder. It is practically insoluble in water (0.082 mg/mL). It is soluble in methanol and dimethyl sulfoxide.

Each MYRBETRIQ (mirabegron extended-release tablets) for oral use contains either 25 mg or 50 mg of mirabegron and the following inactive ingredients: butylated hydroxytoluene, hydroxypropyl cellulose, hypromellose, magnesium stearate, polyethylene glycol, polyethylene oxide, red ferric oxide (25 mg tablet only), and yellow ferric oxide.

Each bottle of MYRBETRIQ Granules (mirabegron for extended-release oral suspension) contains approximately 8.3 g of granules, which contain 830 mg of mirabegron, and the following inactive ingredients: acesulfame potassium, diluted hydrochloric acid, ethylparaben, hypromellose, magnesium stearate, mannitol, methylparaben, silicon dioxide, simethicone, sodium polystyrene sulfonate, and xanthan gum. After reconstituted with 100 mL water, the suspension contains 8 mg/mL of mirabegron.

12 CLINICAL PHARMACOLOGY

12.1 Mechanism of Action

Mirabegron is an agonist of the human beta-3 adrenergic receptor (AR) as demonstrated by in vitro laboratory experiments using the cloned human beta-3 AR. Mirabegron relaxes the detrusor smooth muscle during the storage phase of the urinary bladder fill-void cycle by activation of beta-3 AR which increases bladder capacity. Although mirabegron showed very low intrinsic activity for cloned human beta-1 AR and beta-2 AR, results in humans indicate that beta-1 AR stimulation occurred at a mirabegron dose of 200 mg.

12.2 Pharmacodynamics

Urodynamics

The effects of mirabegron on maximum urinary flow rate and detrusor pressure at maximum flow rate were assessed in a urodynamic study consisting of 200 male patients with lower urinary tract symptoms (LUTS) and BOO. Administration of mirabegron once daily for 12 weeks did not adversely affect the mean maximum flow rate or mean detrusor pressure at maximum flow rate in this study. Nonetheless, mirabegron should be administered with caution to patients with clinically significant BOO [see Warnings and Precautions (5.2)].

Cardiac Electrophysiology

The effect of multiple doses of mirabegron 50 mg, 100 mg, and 200 mg (four times the maximum recommended dose) once daily on QTc interval was evaluated in a randomized, placebo- and active-controlled (moxifloxacin 400 mg), four-treatment arm, parallel crossover study in 352 healthy subjects. In a study with demonstrated ability to detect small effects, the upper bound of the one-sided 95% confidence interval for the largest placebo-adjusted, baseline-corrected QTc based on individual correction method (QTcI) was below 10 msec. For the 50 mg mirabegron dose group (the maximum approved dosage), the mean difference from placebo on QTcI interval at 4 to 5 hours post-dose was 3.7 msec (upper bound of the 95% CI 5.1 msec).

For the mirabegron 100 mg and 200 mg dose groups (dosages greater than the maximum approved dose and resulting in substantial multiples of the anticipated maximum blood levels at 50 mg), the mean differences from placebo in QTcI interval at 4 to 5 hours post dose were 6.1 msec (upper bound of the 95% CI 7.6 msec) and 8.1 msec (upper bound of the 95% CI 9.8 msec), respectively. At the mirabegron 200 mg dose, in females, the mean effect was 10.4 msec (upper bound of the 95% CI 13.4 msec).

In this thorough QT study, mirabegron increased heart rate on ECG in a dose-dependent manner. Maximum mean increases from baseline in heart rate for the 50 mg, 100 mg, and 200 mg dose groups compared to placebo were 6.7 bpm, 11 bpm, and 17 bpm, respectively. In the clinical efficacy and safety studies, the change from baseline in mean pulse rate for mirabegron 50 mg was approximately 1 bpm. In this thorough QT study, mirabegron also increased blood pressure in a dose-dependent manner (see Effects on Blood Pressure).

Effects on Blood Pressure

In a study of 352 healthy subjects assessing the effect of multiple daily doses of 50 mg, 100 mg, and 200 mg (four times the maximum recommended dose) of mirabegron for 10 days on the QTc interval, the maximum mean increase in supine systolic blood pressure (SBP)/diastolic blood pressure (DBP) at the maximum recommended dose of 50 mg was approximately 4.0/1.6 mm Hg greater than placebo [see Warnings and Precautions (5.1)]. The 24-hour average increases in SBP compared to placebo were 3.0, 5.5, and 9.7 mm Hg at mirabegron doses of 50 mg, 100 mg, and 200 mg, respectively. Increases in DBP were also dose-dependent, but were smaller than SBP.

In another study in 96 healthy subjects to assess the impact of age on pharmacokinetics of multiple daily doses of 50 mg, 100 mg, 200 mg, and 300 mg (six times the maximum recommended dose) of mirabegron for 10 days, SBP also increased in a dose-dependent manner. The mean maximum increases in SBP were approximately 2.5, 4.5, 5.5, and 6.5 mm Hg for mirabegron exposures associated with doses of 50 mg, 100 mg, 200 mg, and 300 mg, respectively.

In three, 12-week, double-blind, placebo-controlled, safety and efficacy studies (Studies 1, 2, and 3) in patients with OAB receiving mirabegron 25 mg, 50 mg, or 100 mg (two times the maximum recommended dose) once daily, mean increases in SBP/DBP compared to placebo of approximately 0.5 – 1 mm Hg were observed. Morning SBP increased by at least 15 mm Hg from baseline in 5.3%, 5.1%, and 6.7% of placebo, mirabegron 25 mg and mirabegron 50 mg patients, respectively. Morning DBP increased by at least 10 mm Hg in 4.6%, 4.1%, and 6.6% of placebo, mirabegron 25 mg, and mirabegron 50 mg patients, respectively. Both SBP and DBP increases were reversible upon discontinuation of treatment.

In a 12-week, double-blind, placebo-controlled, safety and efficacy study (Study 6) in patients with OAB receiving mirabegron 25 mg or 50 mg once daily coadministered with solifenacin succinate 5 mg, no consistent differences in 24‑hour mean SBP/DBP were observed compared to placebo, mirabegron or solifenacin succinate monotherapy as assessed with 24-hour Ambulatory Blood Pressure Monitoring (ABPM). Similar frequencies of categorical changes were observed for combination treatment versus placebo in 24‑hour mean SBP/DBP.

Effect on Intraocular Pressure (IOP)

Mirabegron 100 mg once daily did not increase IOP in healthy subjects after 56 days of treatment. In a phase 1 study assessing the effect of mirabegron on IOP using Goldmann applanation tonometry in 310 healthy subjects, a dose of mirabegron 100 mg was non-inferior to placebo for the primary endpoint of the treatment difference in mean change from baseline to day 56 in subject average IOP; the upper bound of the two-sided 95% CI of the treatment difference between mirabegron 100 mg and placebo was 0.3 mm Hg.

12.3 Pharmacokinetics

Absorption
MYRBETRIQ Monotherapy for Adult OAB
After oral administration of mirabegron in healthy volunteers, mirabegron was absorbed to reach maximum plasma concentrations (Cmax) at approximately 3.5 hours. The absolute bioavailability increased from 29% at a dose of 25 mg to 35% at a dose of 50 mg. Mean Cmax and AUC increased more than dose proportionally. This relationship was more apparent at doses above 50 mg. In the overall population of males and females, a 2-fold increase in dose from 50 mg to 100 mg mirabegron increased Cmax and AUCtau by approximately 2.9- and 2.6-fold, respectively, whereas a 4-fold increase in dose from 50 to 200 mg mirabegron increased Cmax and AUCtau by approximately 8.4- and 6.5-fold. Steady-state concentrations were achieved within 7 days of once daily dosing with mirabegron. After once daily administration, plasma exposure of mirabegron at steady-state was approximately double that seen after a single dose.

MYRBETRIQ/MYRBETRIQ Granules for Pediatric Neurogenic Detrusor Overactivity (NDO)
The median Tmax of mirabegron following oral administration of a single dose of MYRBETRIQ or mirabegron for extended-release oral suspension in pediatric patients under fed state was 4-5 hours. Population pharmacokinetic analysis predicted that the median Tmax of MYRBETRIQ or mirabegron for extended-release oral suspension at steady-state was 3-4 hours.

Effect of Food
  MYRBETRIQ Monotherapy for Adult OAB
  There were no clinically significant differences in mirabegron pharmacokinetics when administered with or without food in adult patients.
  MYRBETRIQ/MYRBETRIQ Granules for Pediatric Neurogenic Detrusor Overactivity (NDO)
  In the fasted state, steady-state mirabegron AUC increased by 120% relative to the fed state in pediatric patients
  receiving MYRBETRIQ. Fasted Cmax and AUC increased by 170% and 80%, respectively, compared to the fed state
  following administration of MYRBETRIQ Granules in healthy volunteers.

Distribution
MYRBETRIQ Monotherapy for Adult OAB
Mirabegron is extensively distributed in the body. The volume of distribution at steady-state (Vss) is approximately 1670 L following intravenous administration. Mirabegron is bound (approximately 71%) to human plasma proteins, and shows moderate affinity for albumin and alpha-1 acid glycoprotein. Mirabegron distributes to erythrocytes. Based on an in vitro study, erythrocyte concentrations of ^14C-mirabegron were about 2-fold higher than in plasma.

MYRBETRIQ/MYRBETRIQ Granules for Pediatric Neurogenic Detrusor Overactivity (NDO)

Mirabegron volume of distribution was relatively large in pediatric patients (the range of mean Vz/F under fed state in pediatric patients across studies: 4895-13726 L) and increased with increasing body weight.

Elimination

MYRBETRIQ Monotherapy for Adult OAB

The terminal elimination half-life (t1/2) of mirabegron is approximately 50 hours in patients.

MYRBETRIQ/MYRBETRIQ Granules for Pediatric Neurogenic Detrusor Overactivity (NDO)

The mean terminal elimination half-life (t1/2) of mirabegron is approximately 26 to 31 hours in pediatric patients.

Metabolism
  Mirabegron is metabolized via multiple pathways involving dealkylation, oxidation, (direct) glucuronidation, and amide hydrolysis. Mirabegron is the major circulating component following a single dose of ^14C-mirabegron. Two major metabolites were observed in human plasma and are phase 2 glucuronides representing 16% and 11% of total exposure, respectively. These metabolites are not pharmacologically active toward beta-3 adrenergic receptor. Although, in vitro studies suggest a role for CYP2D6 and CYP3A4 in the oxidative metabolism of mirabegron, in vivo results indicate that these isozymes play a limited role in the overall elimination. In healthy subjects who were genotypically poor metabolizers of CYP2D6, mean Cmax and AUCtau were approximately 16% and 17% higher than in extensive metabolizers of CYP2D6, respectively. In vitro and ex vivo studies have shown the involvement of butylcholinesterase, uridine diphospho-glucuronosyltransferases (UGT), and possibly alcohol dehydrogenase in the metabolism of mirabegron, in addition to CYP3A4 and CYP2D6.
  Excretion
  MYRBETRIQ Monotherapy for Adult OAB
  Total body clearance (CLtot) from plasma is approximately 57 L/h following intravenous administration. Renal clearance (CLR) is approximately 13 L/h, which corresponds to nearly 25% of CLtot. Renal elimination of mirabegron is primarily through active tubular secretion along with glomerular filtration. The urinary elimination of unchanged mirabegron is dose-dependent and ranges from approximately 6.0% after a daily dose of 25 mg to 12.2% after a daily dose of 100 mg. Following the administration of 160 mg ^14C-mirabegron solution to healthy volunteers, approximately 55% of the radioactivity dose was recovered in the urine and 34% in the feces. Approximately 25% of unchanged mirabegron was recovered in urine and 0% in feces.
  MYRBETRIQ/MYRBETRIQ Granules for Pediatric Neurogenic Detrusor Overactivity (NDO)
  Population pharmacokinetic model predicted that mirabegron clearance in pediatric patients increased with body weight.

Specific Populations

Geriatric Patients
  The Cmax and AUC of mirabegron following multiple oral doses in elderly volunteers (≥ 65 years) were similar to those in younger volunteers (18 to 45 years) [see Use in Specific Populations (8.5)].
  Pediatric Patients
  In patients 3 to less than 18 years of age, age was not predicted to affect mirabegron pharmacokinetic parameters after accounting for differences in body weight [see Use in Specific Populations (8.4)].
  Gender
  MYRBETRIQ Monotherapy for Adult OAB
  The Cmax and AUC of mirabegron were approximately 40% to 50% higher in females than in males. When corrected for differences in body weight, the mirabegron systemic exposure was 20%-30% higher in females compared to males.
  MYRBETRIQ/MYRBETRIQ Granules for Pediatric Neurogenic Detrusor Overactivity (NDO)
  Gender has no meaningful impact on mirabegron pharmacokinetics in the pediatric population from 3 to less than 18 years of age.
  Race
  The pharmacokinetics of mirabegron were comparable between Caucasians and African-American Blacks. Cross studies comparison showed that the exposure in Japanese subjects were higher than that in North American subjects. However, when the Cmax and AUC were normalized for dose and body weight, the difference was smaller.
  Patients with Renal Impairment
  Following single-dose administration of 100 mg mirabegron in adult volunteers with mild renal impairment (eGFR 60 to 89 mL/min/1.73 m^2 as estimated by MDRD), mean mirabegron Cmax and AUC were increased by 6% and 31% relative to adult volunteers with normal renal function. In adult volunteers with moderate renal impairment (eGFR 30 to 59 mL/min/1.73 m^2), Cmax and AUC were increased by 23% and 66%, respectively. In adult volunteers with severe renal impairment (eGFR 15 to 29 mL/min/1.73 m^2), mean Cmax and AUC values were 92% and 118% higher compared to healthy subjects with normal renal function. Mirabegron has not been studied in adult patients with End-Stage Renal Disease (ESRD) (eGFR less than 15 mL/min/1.73 m^2) or adult patients requiring dialysis.
  Patients with Hepatic Impairment
  Following single-dose administration of 100 mg mirabegron in adult volunteers with mild hepatic impairment (Child-Pugh Class A), mean mirabegron Cmax and AUC were increased by 9% and 19%, relative to adult volunteers with normal hepatic function. In adult volunteers with moderate hepatic impairment (Child-Pugh Class B), mean Cmax and AUC values were 175% and 65% higher. Mirabegron has not been studied in adult patients with severe hepatic impairment (Child-Pugh Class C).

Drug Interaction Studies

In Vitro Studies
  Effect of Other Drugs on Mirabegron
  Mirabegron is transported and metabolized through multiple pathways. Mirabegron is a substrate for CYP3A4, CYP2D6, butyrylcholinesterase, UGT, the efflux transporter P-glycoprotein (P-gp), and the influx organic cation transporters (OCT) OCT1, OCT2, and OCT3. Sulfonylurea hypoglycemic agents glibenclamide (a CYP3A4 substrate), gliclazide (a CYP2C9 and CYP3A4 substrate), and tolbutamide (a CYP2C9 substrate) did not affect the in vitro metabolism of mirabegron.
  Effect of Mirabegron on Other Drugs
  Studies of mirabegron using human liver microsomes and recombinant human CYP enzymes showed that mirabegron is a moderate and time-dependent inhibitor of CYP2D6 and a weak inhibitor of CYP3A. Mirabegron is unlikely to inhibit the metabolism of coadministered drugs metabolized by the following cytochrome P450 enzymes: CYP1A2, CYP2B6, CYP2C8, CYP2C9, CYP2C19, and CYP2E1 because mirabegron did not inhibit the activity of these enzymes at clinically relevant concentrations. Mirabegron did not induce CYP1A2 or CYP3A. Mirabegron inhibited P-gp-mediated drug transport at high concentrations. Mirabegron is predicted not to cause clinically relevant inhibition of OCT-mediated drug transport. Mirabegron did not affect the metabolism of glibenclamide or tolbutamide.
  Effect of Alcohol on Mirabegron
  The addition of alcohol (5, 10, 20, and 40%) increases the dissolution rate of mirabegron from MYRBETRIQ Granules at pH 6.8. The clinical impact on the systemic exposure of mirabegron has not been evaluated. The addition of alcohol does not increase the dissolution rate of MYRBETRIQ Granules at pH 1.0 or MYRBETRIQ (extended-release tablets) regardless of pH.
  In Vivo Studies
  MYRBETRIQ Monotherapy for Adult OAB
  The effect of coadministered drugs on the pharmacokinetics of mirabegron and the effect of mirabegron on the pharmacokinetics of coadministered drugs was studied after single and multiple doses of mirabegron. Most drug-drug interactions (DDI) were studied using mirabegron 100 mg extended-release tablets. However, interaction studies of mirabegron with metoprolol and with metformin were studied using mirabegron 160 mg immediate-release (IR) tablets.
  The effect of ketoconazole, rifampicin, solifenacin succinate, tamsulosin, and metformin on systemic mirabegron exposure is shown in Figure 1.
  The effect of mirabegron on metoprolol, desipramine, combined oral contraceptive-COC (ethinyl estradiol-EE, levonorgestrel-LNG), solifenacin succinate, digoxin, warfarin, tamsulosin, and metformin is shown in Figure 2.
  In these studies, the largest increase in mirabegron systemic exposure was seen in the ketoconazole DDI study. As a potent CYP3A4 inhibitor, ketoconazole increased mirabegron Cmax by 45% and mirabegron AUC by 80% after multiple dose administration of 400 mg of ketoconazole for 9 days prior to the administration of a single dose of 100 mg mirabegron in 23 male and female healthy subjects.
  As a moderate CYP2D6 inhibitor, mirabegron increased the systemic exposure to metoprolol and desipramine:
  • Mirabegron increased the Cmax of metoprolol by 90% and metoprolol AUC by 229% after multiple doses of 160 mg mirabegron IR tablets once daily for 5 days and a single dose of 100 mg metoprolol tablet in 12 healthy male subjects administered before and concomitantly with mirabegron.
  • Mirabegron increased the Cmax of desipramine by 79% and desipramine AUC by 241% after multiple dose administration of 100 mg mirabegron once daily for 18 days and a single dose of 50 mg desipramine before and concomitantly with mirabegron in 28 male and female healthy subjects.
  The effect on the pharmacokinetics of coadministered digoxin and tamsulosin was studied after multiple doses of a combination of mirabegron and solifenacin succinate. Concomitant administration of 0.25 mg digoxin with a combination of 5 mg solifenacin succinate and 50 mg mirabegron increased digoxin AUCtau and Cmax by approximately 10% and 14%, respectively. Concomitant administration of 0.4 mg tamsulosin with a combination of 5 mg solifenacin succinate and 50 mg mirabegron increased tamsulosin AUCtau and Cmax by 47.5% and 54.3%, respectively. The observed changes in the pharmacokinetics of tamsulosin are in line with cytochrome P450 inhibition as shown by coadministration with mirabegron alone.
  Figures 1 and 2 show the magnitude of these interactions on the pharmacokinetic parameters and the recommendations for dose adjustment, if any:

Figure 1: The Effect of Coadministered Drugs on Exposure of MYRBETRIQ and Dose Recommendation

(1) Although no dose adjustment is recommended with solifenacin succinate or tamsulosin based on the lack of pharmacokinetic interaction, MYRBETRIQ should be administered with caution to patients taking muscarinic antagonist medications for the treatment of OAB and in patients with clinically significant BOO because of the risk of urinary retention [see Warnings and Precautions (5.2)].

Figure 2: The Effect of MYRBETRIQ on Exposure of Coadministered Medication

(1) Since mirabegron is a moderate CYP2D6 inhibitor, the systemic exposure to CYP2D6 substrates such as metoprolol and desipramine is increased when coadministered with mirabegron. Therefore, appropriate monitoring and dose adjustment may be necessary, especially with narrow therapeutic index CYP2D6 substrates, such as thioridazine, flecainide, and propafenone [see Warnings and Precautions (5.4) and Drug Interactions (7.1)].
  (2) For patients who are initiating a combination of mirabegron and digoxin, the lowest dose for digoxin should initially be prescribed. Serum digoxin concentrations should be monitored and used for titration of the digoxin dose to obtain the desired clinical effect [see Drug Interactions (7.2)]. The same approach for the dose of digoxin should be followed when digoxin is coadministered with mirabegron and solifenacin succinate.
  (3) Warfarin was administered as a single 25 mg dose of the racemate (a mixture of R-warfarin and S-warfarin). Based on this single-dose study, mirabegron had no effect on the warfarin pharmacodynamic endpoints such as INR and prothrombin time. However, the effect of mirabegron on multiple doses of warfarin and on warfarin pharmacodynamic end points such as INR and prothrombin time has not been fully investigated [see Drug Interactions (7.3)].
  (4) Although no dose adjustment is recommended with solifenacin succinate or tamsulosin based on the lack of pharmacokinetic interaction, MYRBETRIQ should be administered with caution to patients taking muscarinic antagonist medications for the treatment of OAB and in BOO because of the risk of urinary retention [see Warnings and Precautions (5.2)].
  Based on the lack of relevant pharmacokinetic interaction, no dose adjustment for tamsulosin is recommended when coadministered with mirabegron and solifenacin succinate.

13 NONCLINICAL TOXICOLOGY

13.1 Carcinogenesis, Mutagenesis, Impairment of Fertility

Carcinogenicity

Long-term carcinogenicity studies were conducted in rats and mice dosed orally with mirabegron for two years. Male rats were dosed at 0, 12.5, 25, or 50 mg/kg/day and female rats and both sexes of mice were dosed at 0, 25, 50, or 100 mg/kg/day. Mirabegron showed no carcinogenic potential at systemic exposures (AUC) 38 to 45-fold higher than the MRHD in rats and 21 to 38-fold higher than the MRHD in mice than the human systemic exposure at the 50 mg dose.
Mutagenesis
Mirabegron was not mutagenic in the Ames bacterial reverse mutation assay, did not induce chromosomal aberrations in human peripheral blood lymphocytes at concentrations that were not cytotoxic, and was not clastogenic in the rat micronucleus assay.
Impairment of Fertility
Fertility studies in rats showed that mirabegron had no effect on either male or female fertility at non-lethal doses up to 100 mg/kg/day. Systemic exposures (AUC) at 100 mg/kg in female rats was estimated to be 22-fold the MRHD in women and 93-fold the MRHD in men.

14 CLINICAL STUDIES

14.1 MYRBETRIQ Monotherapy for Adult OAB

MYRBETRIQ was evaluated in three, 12-week, double-blind, randomized, placebo-controlled, parallel group, multicenter clinical trials in patients with overactive bladder with symptoms of urge urinary incontinence, urgency, and urinary frequency (Studies 1, 2, and 3). Entry criteria required that patients had symptoms of overactive bladder for at least 3 months duration, at least 8 micturitions per day, and at least 3 episodes of urgency with or without incontinence over a 3-day period. The majority of patients were Caucasian (94%) and female (72%) with a mean age of 59 years (range 18 – 95 years). The population included both naïve patients who had not received prior muscarinic antagonist pharmacotherapy for overactive bladder (48%) and those who had received prior muscarinic antagonist pharmacotherapy for OAB (52%).
In Study 1 (NCT00689104), patients were randomized to placebo, MYRBETRIQ 50 mg, MYRBETRIQ 100 mg, or an active control once daily. In Study 2 (NCT00662909), patients were randomized to placebo, MYRBETRIQ 50 mg or MYRBETRIQ 100 mg once daily. In Study 3 (NCT00912964), patients were randomized to placebo, MYRBETRIQ 25 mg or MYRBETRIQ 50 mg once daily.
The co-primary efficacy endpoints in all 3 trials were (1) change from baseline to end of treatment (Week 12) in mean number of incontinence episodes per 24 hours and (2) change from baseline to end of treatment (Week 12) in mean number of micturitions per 24 hours, based on a 3-day micturition diary. An important secondary endpoint was the change from baseline to end of treatment (Week 12) in mean volume voided per micturition.
Results for the co-primary endpoints and mean volume voided per micturition from Studies 1, 2, and 3 are shown in Table 13.

Table 13: Mean Baseline and Change from Baseline at Week 12 [Week 12 is the last observation on treatment.] for Incontinence Episodes, Micturition Frequency, and Volume Voided per Micturition in Patients with Overactive Bladder in Studies 1, 2, and 3
Parameter | Study 1 |  | Study 2 |  | Study 3
 | Placebo | MYRBETRIQ 50 mg | Placebo | MYRBETRIQ 50 mg | Placebo | MYRBETRIQ 25 mg | MYRBETRIQ 50 mg
Number of Incontinence Episodes per 24 Hours [For incontinence episodes per 24 hours, the analysis population is restricted to patients with at least 1 episode of incontinence at baseline.]
n | 291 | 293 | 325 | 312 | 262 | 254 | 257
Baseline (mean) | 2.67 | 2.83 | 3.03 | 2.77 | 2.43 | 2.65 | 2.51
Change from baseline (adjusted mean [Least squares mean adjusted for baseline, gender, and geographical region.]) | -1.17 | -1.57 | -1.13 | -1.47 | -0.96 | -1.36 | -1.38
Difference from placebo (adjusted mean) | -- | -0.41 | -- | -0.34 | -- | -0.40 | -0.42
95% Confidence Interval | -- | (-0.72, -0.09) | -- | (-0.66, -0.03) | -- | (-0.74, -0.06) | (-0.76, -0.08)
p-value | -- | 0.003 [Statistically significantly superior compared to placebo at the 0.05 level with multiplicity adjustment.] | -- | 0.026 | -- | 0.005 | 0.001
Number of Micturitions per 24 Hours
n | 480 | 473 | 433 | 425 | 415 | 410 | 426
Baseline (mean) | 11.71 | 11.65 | 11.51 | 11.80 | 11.48 | 11.68 | 11.66
Change from baseline (adjusted mean) | -1.34 | -1.93 | -1.05 | -1.66 | -1.18 | -1.65 | -1.60
Difference from placebo (adjusted mean) | -- | -0.60 | -- | -0.61 | -- | -0.47 | -0.42
95% Confidence Interval | -- | (-0.90, -0.29) | -- | (-0.98, -0.24) | -- | (-0.82, -0.13) | (-0.76, -0.08)
p-value | -- | < 0.001 | -- | 0.001 | -- | 0.007 | 0.015
Volume Voided (mL) per Micturition
n | 480 | 472 | 433 | 424 | 415 | 410 | 426
Baseline (mean) | 156.7 | 161.1 | 157.5 | 156.3 | 164.0 | 165.2 | 159.3
Change from baseline (adjusted mean) | 12.3 | 24.2 | 7.0 | 18.2 | 8.3 | 12.8 | 20.7
Difference from placebo (adjusted mean) | -- | 11.9 | -- | 11.1 | -- | 4.6 | 12.4
95% Confidence Interval | -- | (6.3, 17.4) | -- | (4.4, 17.9) | -- | (-1.6, 10.8) | (6.3, 18.6)
p-value | -- | < 0.001 | -- | 0.001 | -- | 0.15 | < 0.001

MYRBETRIQ 25 mg was effective in treating the symptoms of OAB within 8 weeks and MYRBETRIQ 50 mg was effective in treating the symptoms of OAB within 4 weeks. Efficacy of both 25 mg and 50 mg doses of MYRBETRIQ was maintained through the 12-week treatment period.

Figures 3 through 8 show the co-primary endpoints, mean change from baseline (BL) over time in number of incontinence episodes per 24 hours, and mean change from baseline over time in number of micturitions per 24 hours, in Studies 1, 2, and 3.

Figure 3: Mean (SE) Change from Baseline in Mean Number of Incontinence Episodes per 24 Hours – Study 1
Figure 4: Mean (SE) Change from Baseline in Mean Number of Micturitions per 24 Hours – Study 1
Figure 5: Mean (SE) Change from Baseline in Mean Number of Incontinence Episodes per 24 Hours – Study 2
Figure 6: Mean (SE) Change from Baseline in Mean Number of Micturitions per 24 Hours – Study 2
Figure 7: Mean (SE) Change from Baseline in Mean Number of Incontinence Episodes per 24 Hours – Study 3
Figure 8: Mean (SE) Change from Baseline in Mean Number of Micturitions per 24 Hours – Study 3

14.2 MYRBETRIQ Combination Therapy for Adult OAB

Coadministration of MYRBETRIQ with Solifenacin Succinate

Coadministration of MYRBETRIQ with solifenacin succinate was evaluated in a 12-week, double-blind, randomized, placebo-controlled, parallel group, multicenter clinical trial in patients with OAB with symptoms of urge urinary incontinence, urgency, and urinary frequency (Study 6). Entry criteria required that patients had symptoms of OAB for at least 3 months duration, on average at least 8 micturitions and at least 1 urgency episode per day, and at least 3 episodes of incontinence, over a 7-day period. The majority of patients were Caucasian (80%) and female (77%) with a mean age of 57 years (range 18 to 86 years). The population included both naïve patients who had not received prior pharmacotherapy for OAB (54%) and those who had received prior pharmacotherapy for OAB (46%).

In Study 6 (NCT01972841), patients were randomized to placebo, solifenacin succinate 5 mg, MYRBETRIQ 25 mg, MYRBETRIQ 50 mg, solifenacin succinate 5 mg plus MYRBETRIQ 25 mg, or solifenacin succinate 5 mg plus MYRBETRIQ 50 mg once daily.

The co-primary efficacy endpoints in Study 6 were (1) change from baseline to end of treatment (week 12) in mean number of incontinence episodes per 24 hours and (2) change from baseline to end of treatment (week 12) in mean number of micturitions per 24 hours, based on a 7-day micturition diary. An important secondary endpoint was the change from baseline to end of treatment (week 12) in mean volume voided per micturition.

Results for the co-primary endpoints and mean volume voided per micturition for the overall patient population from Study 6 are shown in Table 14.

Table 14: Mean Baseline and Change from Baseline at Week 12 [Week 12 is the last observation on treatment.] for Incontinence Episodes, Micturition Frequency, and Volume Voided per Micturition Overall Population with Overactive Bladder in Study 6
Parameter | Placebo | MYRBETRIQ; 25 mg | MYRBETRIQ; 50 mg | Solifenacin Succinate; 5 mg | MYRBETRIQ 25 mg; +; Solifenacin Succinate 5 mg | MYRBETRIQ 50 mg; +; Solifenacin Succinate 5 mg
Number of Incontinence Episodes per 24 Hours
n | 412 | 409 | 406 | 413 | 823 | 816
Baseline (mean) | 3.40 | 3.42 | 3.16 | 3.59 | 3.21 | 3.15
Change from baseline; (adjusted mean [Least squares mean adjusted for baseline, gender, age group (< 65, ≥ 65 years), previous OAB medication (yes, no), and geographical region using an ANCOVA model.]) | -1.34 | -1.70 | -1.76 | -1.79 | -2.04 | -1.98
Difference from; Solifenacin Succinate; (adjusted mean) | -- | -- | -- | -- | -0.25 | -0.20
95% Confidence Interval | -- | -- | -- | -- | (-0.49, -0.01) | (-0.44, 0.04)
Difference from; MYRBETRIQ; (at the same MYRBETRIQ dose, adjusted mean) | -- | -- | -- | -- | -0.34 | -0.23
95% Confidence Interval | -- | -- | -- | -- | (-0.58, -0.10) | (-0.47, 0.01)
Number of Micturitions per 24 Hours
n | 412 | 409 | 406 | 413 | 823 | 816
Baseline (mean) | 10.97 | 10.81 | 11.19 | 10.74 | 10.72 | 10.72
Change from baseline; (adjusted mean) | -1.64 | -2.00 | -2.03 | -2.20 | -2.49 | -2.59
Difference from; Solifenacin Succinate; (adjusted mean) | -- | -- | -- | -- | -0.29 | -0.39
95% Confidence Interval | -- | -- | -- | -- | (-0.57, -0.01) | (-0.67, -0.11)
Difference from; MYRBETRIQ; (at the same MYRBETRIQ dose, adjusted mean) | -- | -- | -- | -- | -0.48 | -0.56
95% Confidence Interval | -- | -- | -- | -- | (-0.76, -0.21) | (-0.84, -0.28)
Volume Voided (mL) per Micturition
n | 413 | 407 | 408 | 411 | 821 | 821
Baseline (mean) | 157.82 | 152.46 | 155.35 | 151.86 | 159.19 | 153.83
Change from baseline; (adjusted mean) | 8.44 | 13.32 | 21.99 | 30.99 | 34.84 | 39.73
Difference from; Solifenacin Succinate; (adjusted mean) | -- | -- | -- | -- | 3.85 | 8.75
95% Confidence Interval | -- | -- | -- | -- | (-2.29, 10.00) | (2.61, 14.89)
Difference from; MYRBETRIQ; (at the same MYRBETRIQ dose, adjusted mean) | -- | -- | -- | -- | 21.52 | 17.74
95% Confidence Interval | -- | -- | -- | -- | (15.35, 27.68) | (11.58, 23.90)
ANCOVA: Analysis of covariance

Figures 9 and 10 show the co-primary endpoints, mean change from baseline (BL) over time in number of incontinence episodes per 24 hours, and mean change from baseline over time in number of micturitions per 24 hours, in the overall patient population in Study 6.

Figure 9: Mean Change from Baseline in Mean (± SE) Number of Incontinence Episodes per 24 Hours at Each Visit (FAS) – Study 6
Figure 10: Mean Change from Baseline in Mean (± SE) Number of Micturitions per 24 Hours at Each Visit (FAS) – Study 6

MYRBETRIQ as Add-on Therapy to Solifenacin Succinate

MYRBETRIQ add-on therapy to solifenacin succinate was evaluated in one, 12-week, double-blind, randomized, active‑controlled, multicenter clinical trial in incontinent OAB patients who received solifenacin succinate for 4 weeks and required additional relief for their OAB symptoms (Study 7). Entry criteria required that patients had symptoms of OAB for at least 3 months duration (urge urinary incontinence, urgency, and urinary frequency), and at least 1 incontinence episode during a 3-day period after being treated with solifenacin succinate 5 mg for 4 weeks. The majority of patients were Caucasian (94%) and female (83%) with a mean age of 57 years (range 18 to 89 years). Patients were randomized to solifenacin succinate 5 mg, solifenacin succinate 10 mg, or solifenacin succinate 5 mg plus MYRBETRIQ 25 mg once daily. After 4 weeks, all patients in the combination treatment arm had a dose increase from MYRBETRIQ 25 mg to MYRBETRIQ 50 mg.

The primary efficacy endpoint in Study 7 (NCT01908829) was change from baseline to end of treatment (week 12) in mean number of incontinence episodes per 24 hours. Two important secondary endpoints were change from baseline to end of treatment in mean number of micturitions per 24 hours and change from baseline to end of treatment in mean volume voided per micturition. Results for the primary and additional endpoints from Study 7 are shown in Table 15.

Table 15: Change from Baseline at Week 12 [Week 12 is the last observation on treatment.] for Incontinence Episodes, Micturition Frequency, and Volume Voided per Micturition in Patients with Overactive Bladder in Study 7
Parameter | Solifenacin Succinate; 5 mg | MYRBETRIQ; 25 mg/50 mg; +; Solifenacin; Succinate; 5 mg
Number of Incontinence Episodes per 24 Hours
n | 704 | 706
Baseline (mean) | 3.15 | 3.24
Change from baseline (adjusted mean [Least squares mean adjusted for baseline, gender, age group (< 65, ≥ 65 years), geographical region, and 4-week incontinence reduction group using ANCOVA model.]) | -1.53 | -1.80
Difference (MYRBETRIQ + Solifenacin Succinate) from Solifenacin Succinate (adjusted mean [Differences of adjusted means are calculated by subtracting the adjusted mean of solifenacin succinate monotherapy groups from adjusted mean of MYRBETRIQ + Solifenacin Succinate group based on ANCOVA model described above.]) | -0.26 | --
95% Confidence Interval | (-0.47, -0.05) | --
Number of Micturitions per 24 Hours
n | 704 | 706
Baseline (mean) | 8.90 | 9.13
Change from baseline (adjusted mean) | -1.14 | -1.59
Difference (MYRBETRIQ + Solifenacin Succinate) from Solifenacin Succinate (adjusted mean) | -0.45 (0.12) | --
95% Confidence Interval | (-0.67, -0.22) | --
Volume Voided (mL) per Micturition
n | 682 | 680
Baseline (mean) | 170.92 | 172.93
Change from baseline (adjusted mean) | 16.52 | 28.05
Difference (MYRBETRIQ + Solifenacin Succinate) from Solifenacin Succinate (adjusted mean) | 11.52 | --
95% Confidence Interval | (6.06, 16.99)
ANCOVA: Analysis of covariance

Long-term Coadministration of MYRBETRIQ with Solifenacin Succinate

Long-term efficacy of coadministration of MYRBETRIQ 50 mg with solifenacin succinate 5 mg was evaluated in a 52-week, double-blind, randomized, active-controlled, parallel group, multicenter clinical trial in patients with OAB Study 8 (NCT02045862). The primary objective of this study was to evaluate the safety and tolerability of long-term combination treatment and the evaluation of efficacy was the secondary objective of the study. Entry criteria included patients who had completed Study 6 or Study 7 or new patients. All patients had symptoms of OAB for at least 3 months duration, on average at least 8 micturitions and at least 1 urgency episode per day, and at least 3 episodes of incontinence over a 7-day period. Patients were randomized to solifenacin succinate 5 mg, MYRBETRIQ 50 mg, or solifenacin succinate 5 mg plus MYRBETRIQ 50 mg once daily.

Primary efficacy variables were change from baseline to end of treatment in mean number of incontinence episodes per 24 hours and change from baseline to end of treatment in mean number of micturitions per 24 hours. Combination treatment with MYRBETRIQ and solifenacin succinate demonstrated statistically significant greater improvements from baseline compared to MYRBETRIQ 50 mg and solifenacin succinate 5 mg for both efficacy endpoints. The improvements from baseline observed with coadministration of MYRBETRIQ 50 mg and solifenacin succinate 5 mg compared to MYRBETRIQ 50 mg and solifenacin succinate 5 mg were demonstrated at 3 months and were maintained throughout the 1‑year treatment period. Also, for the secondary efficacy variable of change from baseline to end of treatment in mean volume voided (MVV) per micturition, the increase in MVV was statistically significantly greater for combination treatment compared to the MYRBETRIQ 50 mg and solifenacin succinate 5 mg groups.

14.3 MYRBETRIQ/MYRBETRIQ Granules for Pediatric Neurogenic Detrusor Overactivity (NDO)

The efficacy of MYRBETRIQ/MYRBETRIQ Granules was evaluated in Study 9 (NCT02751931), a 52-week, open-label, baseline-controlled, multicenter, dose titration study in pediatric patients 3 years of age and older for the treatment of neurogenic detrusor overactivity (NDO). Study 9 included patients 3 to 17 years of age. Entry criteria required that patients had a diagnosis of neurogenic detrusor overactivity (NDO) with involuntary detrusor contractions with detrusor pressure increase greater than 15 cm H2O and that patients or their caregivers practiced clean intermittent catheterization (CIC). MYRBETRIQ/MYRBETRIQ Granules were administered orally once daily. All patients initially received a weight-based starting dose equivalent to 25 mg daily dose followed by dose titration to a dose equivalent of 50 mg daily dose. The duration of the dose titration period was up to 8 weeks and this period was followed by a dose maintenance period that continued for the duration of the 52-week study.

In Study 9, a total of 86 patients 3 to 17 years of age received MYRBETRIQ/MYRBETRIQ Granules. Of these, 71 patients completed treatment through week 24 and 70 completed 52 weeks of treatment. A total of 68 patients (43 patients 3 to less than 12 years of age and 25 patients 12 to 17 years of age) had valid urodynamic measurements for evaluation of efficacy. The study population included 39 males (45%) and 47 females (55%). The optimized maintenance dose within this study population included 94% of patients at the maximum dose, and 6% of patients at the starting dose.

The primary efficacy endpoint was change from baseline in the patients’ maximum cystometric (bladder) capacity (MCC) after 24 weeks of treatment with MYRBETRIQ/MYRBETRIQ Granules. As shown in Table 16, improvements in MCC were observed in patients 3 to less than 12 years of age and in patients 12 to 17 years of age. The magnitude of the observed changes from baseline in the primary and secondary efficacy endpoints were comparable between patients 3 to less than 12 years of age and patients 12 to 17 years of age.

Table 16: Change from Baseline in Maximum Cystometric Capacity (MCC) at 24 Weeks in Pediatric Patients with Neurogenic Detrusor Overactivity (NDO) Treated with MYRBETRIQ/MYRBETRIQ Granules in Study 9
Parameter |  | Children; Aged 3 to Less than 12 Years; (N=43) [N is the number of patients who took at least one dose and provided valid values for MCC at Baseline and Week 24.]; Mean (SD) | Adolescents; Aged 12 to 17 Years; (N=25); Mean (SD)
Maximum Cystometric Capacity (mL)
 | Baseline; Week 24; Change from baseline; 95% CI | 159 (95); 231 (129); 72 (87); (45, 99) | 239 (99); 352 (125); 113 (83); (79, 147)

Secondary efficacy endpoints from Study 9 for MYRBETRIQ/MYRBETRIQ Granules in pediatric patients with neurogenic detrusor overactivity (NDO) are shown below in Table 17 and Table 18.

Table 17: Changes from Baseline in Other Urodynamic Parameters at Week 24 in Pediatric Patients with Neurogenic Detrusor Overactivity (NDO) Treated with MYRBETRIQ/MYRBETRIQ Granules in Study 9
Parameter | Children; Aged 3 to Less than 12 Years; (N=43) [N is the number of patients who took at least one dose and provided valid values for MCC at Baseline and Week 24.]; Mean (SD) | Adolescents; Aged 12 to 17 Years; (N=25); Mean (SD)
Bladder Compliance (mL/cm H2O) [Number of patients (Children/Adolescents) with data available for both Baseline and Week 24; Bladder Compliance: n=33/21; Number of Overactive Detrusor Contractions: n=36/22; Bladder Volume Prior To First Detrusor Contraction: n=38/24.]
Baseline Change from baseline
Baseline Change from baseline | 16.0 (55.8); 14.6 (42.1); 95% CI: -0.3, 29.5 | 11.1 (10.7); 13.6 (15.0); 95% CI: 6.7, 20.4
Number of Overactive Detrusor Contractions (> 15 cm H2O)
Baseline Change from baseline
Baseline Change from baseline | 3.0 (4.0); -1.9 (4.2); 95% CI: -3.3, -0.4 | 2.1 (3.1); -0.8 (3.9); 95% CI: -2.5, 0.9
Bladder Volume Prior To First Detrusor Contraction (> 15 cm H2O)
Baseline Change from baseline | 115 (83); 93 (88); 95% CI: 64, 122 | 177 (117); 121 (160); 95% CI: 54, 189

Table 18: Changes from Baseline in Maximum Catheterized Urine Volume and Number of Leakage Episodes at Week 24 in Pediatric Patients with Neurogenic Detrusor Overactivity (NDO) Treated with MYRBETRIQ/MYRBETRIQ Granules in Study 9
Parameter | Children; Aged 3 to Less than 12 Years; (N=43) [N is the number of patients who took at least one dose and provided valid values for MCC at Baseline and Week 24.]; Mean (SD) | Adolescents; Aged 12 to 17 Years; (N=25); Mean (SD)
Maximum Catheterized Urine Volume per Day (mL) [Number of patients (Children/Adolescents) with data available for both Baseline and Week 24; Maximum Catheterized Urine Volume per Day: n=41/23; Number of Leakage Episodes per Day: n=26/21.]
Baseline Change from baseline
Baseline Change from baseline | 304 (109); 50 (104); 95% CI: 17, 83 | 360 (111); 84 (122); 95% CI: 32, 137
Number of Leakage Episodes per Day
Baseline Change from baseline | 2.8 (3.7); -2.0 (3.2); 95% CI: -3.2, -0.7 | 1.8 (1.7); -1.0 (1.1); 95% CI: -1.5, -0.5

16 HOW SUPPLIED/STORAGE AND HANDLING

16.1 MYRBETRIQ (mirabegron extended-release tablets)

MYRBETRIQ is supplied as oval, film-coated, extended-release tablets, available in bottles as follows:

Strength | 25 mg | 50 mg
Shape/Color | Oval/Brown | Oval/Yellow
Branding on Tablet | logo, 325 | logo, 355
Bottles of 30 | NDC 0469-2601-30 | NDC 0469-2602-30
Bottles of 90 | NDC 0469-2601-90 | NDC 0469-2602-90

Store and Dispense
Store at 20°C to 25°C (68°F to 77°F) with excursions permitted from 15°C to 30°C (59°F to 86°F) [see USP Controlled Room Temperature].

16.2 MYRBETRIQ Granules (mirabegron for extended-release oral suspension)

MYRBETRIQ Granules (mirabegron for extended-release oral suspension) is supplied as granules in bottles with a child-resistant cap packaged in an aluminum pouch with desiccant. Each bottle is filled with approximately 8.3 g of yellowish white granules, which contain 830 mg of mirabegron. After reconstitution with 100 mL water, the oral suspension is pale brownish yellow to yellow with 8 mg/mL of mirabegron.

1 Carton Containing 1 Bottle | NDC 0469-5020-99

Store and Dispense

Store MYRBETRIQ Granules at 20°C to 25°C (68°F to 77°F) with excursions permitted from 15°C to 30°C (59°F to 86°F) [see USP Controlled Room Temperature].

Store the reconstituted suspension at 20°C to 25°C (68°F to 77°F) for up to 28 days. Discard the unused portion after 28 days.

17 PATIENT COUNSELING INFORMATION

Advise the patient and/or caregiver to read the FDA-approved patient labeling (Patient Information).

Increases in Blood Pressure

Inform patients and/or their caregivers that MYRBETRIQ/MYRBETRIQ Granules may increase blood pressure. Advise patients, especially patients with hypertension, to periodically monitor their blood pressure and report increased measurement to their health care provider [see Warnings and Precautions (5.1)].

Urinary Retention

Inform patients and/or their caregivers that MYRBETRIQ may cause urinary retention in adult patients with bladder outlet obstruction and in patients taking muscarinic antagonist medications for the treatment of OAB. Advise patients to contact their physician if they experience these effects while taking MYRBETRIQ [see Warnings and Precautions (5.2)].

Angioedema

Inform patients and/or their caregivers that MYRBETRIQ/MYRBETRIQ Granules may cause angioedema. Advise patients and/or their caregivers to promptly discontinue MYRBETRIQ/MYRBETRIQ Granules and seek medical attention if angioedema associated with the upper airway swelling occurs as this may be life-threatening [see Warnings and Precautions (5.3)].

Drug Interactions

Advise patients to report their use of any other prescription or nonprescription medications or dietary supplements because co-administration with MYRBETRIQ/MYRBETRIQ Granules may require a dose adjustment and/or increased monitoring of these drugs [see Drug Interactions (7)].

Administration Instructions

MYRBETRIQ

Advise adult patients to swallow MYRBETRIQ whole with water and not to chew, divide, or crush. Advise adult patients to take MYRBETRIQ with or without food.

Advise pediatric patients and/or their caregivers to swallow MYRBETRIQ whole with water and not to chew, divide, or crush. Advise pediatric patients to take MYRBETRIQ with food.

MYRBETRIQ Granules

Advise pediatric patients and/or their caregivers to use an appropriate measuring device and instructions for measuring the correct dose of MYRBETRIQ Granules for extended-release oral suspension. Instruct patients or their caregivers that patients should take MYRBETRIQ Granules for extended-release oral suspension orally within 1 hour after preparation with food once daily and not save the dose for later.

The bottle should be shaken for 1 minute each day if the suspension will not be used for 2 or more days. When ready to use, shake the bottle vigorously for 1 minute then let it stand until the foam on top of the suspension is gone (approximately 1 to 2 minutes).

Missed Dose

Instruct patients and/or their caregivers to take any missed doses as soon as they remember, unless more than 12 hours have passed since the missed dose. If more than 12 hours have passed, the missed dose can be skipped and the next dose should be taken at the usual time.

Marketed and Distributed by:
Astellas Pharma US, Inc.
Northbrook, IL 60062

MYRBETRIQ is a registered trademark of Astellas Pharma Inc. All other trademarks are the property of their respective owners.

© 2012 – 2021 Astellas Pharma US, Inc.

Patient Information

MYRBETRIQ® (meer-BEH-trick)

(mirabegron extended-release tablets) for oral use

MYRBETRIQ® (meer-BEH-trick) GRANULES

(mirabegron for extended-release oral suspension)

What are MYRBETRIQ tablets and MYRBETRIQ GRANULES?

Adults

- MYRBETRIQ tablets is a prescription medicine that can be used alone or with solifenacin succinate to treat adults with the following symptoms due to a condition called overactive bladder (OAB):
  - Urge urinary incontinence: a strong need to urinate with leaking or wetting accidents
  - Urgency: a strong need to urinate right away
  - Frequency: urinating often

Children

- MYRBETRIQ tablets is a prescription medicine used to treat children 3 years of age and older weighing at least 77 pounds (35 kg), with a condition called neurogenic detrusor overactivity (NDO).
- MYRBETRIQ GRANULES is a prescription medicine used to treat children 3 years of age and older with a condition called neurogenic detrusor overactivity (NDO).

It is not known if MYRBETRIQ tablets and MYRBETRIQ GRANULES to treat NDO, are safe and effective in children under 3 years of age.

Who should not take MYRBETRIQ tablets or MYRBETRIQ GRANULES?

Do not take MYRBETRIQ tablets or MYRBETRIQ GRANULES if you are allergic to mirabegron or any of the ingredients in MYRBETRIQ tablets or MYRBETRIQ GRANULES. See the end of this Patient Information leaflet for a complete list of ingredients in MYRBETRIQ tablets and MYRBETRIQ GRANULES.

Before you take MYRBETRIQ tablets or MYRBETRIQ GRANULES, tell your doctor about all of your medical conditions, including if you:

- have liver problems.
- have kidney problems.
- have very high uncontrolled blood pressure.
- have trouble emptying your bladder or you have a weak urine stream.
- are pregnant or plan to become pregnant. It is not known if MYRBETRIQ tablets or MYRBETRIQ GRANULES will harm your unborn baby. Talk to your doctor if you are pregnant or plan to become pregnant.
- are breastfeeding or plan to breastfeed. It is not known if MYRBETRIQ tablets or MYRBETRIQ GRANULES passes into your breast milk. Talk to your doctor about the best way to feed your baby if you take MYRBETRIQ tablets or MYRBETRIQ GRANULES.

Tell your doctor about all the medicines you take, including prescription and over-the-counter medicines, vitamins, and herbal supplements. MYRBETRIQ tablets and MYRBETRIQ GRANULES may affect the way other medicines work, and other medicines may affect how MYRBETRIQ tablets and MYRBETRIQ GRANULES work.

Especially tell your doctor if you take:

- thioridazine (Mellaril or Mellaril-S)
- flecainide (Tambocor)
- propafenone (Rythmol)
- digoxin (Lanoxin)
- solifenacin succinate (VESIcare)

How should I take MYRBETRIQ tablets?

- Take MYRBETRIQ tablets exactly as your doctor tells you to take it.
- You should take 1 MYRBETRIQ tablet 1 time a day.
- If your doctor prescribes MYRBETRIQ tablets and solifenacin succinate together, you should take 1 MYRBETRIQ tablet and 1 solifenacin succinate tablet at the same time, 1 time a day.
- You should take MYRBETRIQ tablets with water and swallow the tablet whole.
- Do not chew, break, or crush the tablet.
- Adults can take MYRBETRIQ tablets with or without food.
- Adults can take MYRBETRIQ tablets and solifenacin succinate together with or without food.
- Children should take MYRBETRIQ tablets with food.
- If you miss a dose of MYRBETRIQ tablets, take it as soon as possible. If it has been more than 12 hours since taking the last dose of MYRBETRIQ tablets, skip that dose and take the next dose at the usual time.
- If you take too much MYRBETRIQ tablets, call your doctor or go to the nearest hospital emergency room right away.

How should I take MYRBETRIQ GRANULES?

- You or your child should take MYRBETRIQ GRANULES exactly as the doctor tells you to take it.
- You or your child should take MYRBETRIQ GRANULES by mouth 1 time a day.
- You or your child should take MYRBETRIQ GRANULES with food.
- You or your child should take MYRBETRIQ GRANULES immediately after preparation (see the steps below). Do not save the dose for later use.
- If you or your child misses a dose of MYRBETRIQ GRANULES, take or give it as soon as possible. If it has been more than 12 hours since the last dose of MYRBETRIQ GRANULES, skip that dose and take or give the next dose at the usual time.
- If you or your child takes too much MYRBETRIQ GRANULES, call your doctor or go to the nearest hospital emergency room right away.

Note: You will receive MYRBETRIQ GRANULES from the pharmacy as a suspension. The suspension is prepared by your pharmacist. You will receive an oral dosing device with the suspension. If the suspension will not be used for 2 or more days, shake the bottle vigorously for 1 minute each day to make sure the granules are mixed well (dispersed). Talk to your pharmacist if you have any questions.
Steps to prepare and take the suspension:
Step 1. Shake the bottle vigorously for 1 minute then let it stand until the foam on top of the suspension is gone (approximately 1 to 2 minutes). If the granules have not mixed well (dispersed), shake the bottle vigorously again for 1 minute and let it stand until the foam is gone.
Step 2. Using the oral dosing device provided by the pharmacist, place the dose into the oral dosing device and take the suspension within 1 hour with food. Disregard any bubbles.
Step 3. After each use, wash the oral dosing device with mild household detergent, rinse under running tap water, and allow it to air dry.

What are the possible side effects of MYRBETRIQ tablets and MYRBETRIQ GRANULES?

MYRBETRIQ tablets and MYRBETRIQ GRANULES may cause serious side effects, including:

- increased blood pressure. MYRBETRIQ tablets and MYRBETRIQ GRANULES may cause your blood pressure to increase or make your blood pressure worse if you have a history of high blood pressure. You and your doctor should check your blood pressure while you are taking MYRBETRIQ tablets or MYRBETRIQ GRANULES. Call your doctor if you have increased blood pressure.
- inability to empty your bladder (urinary retention). MYRBETRIQ tablets may increase your chances of not being able to empty your bladder if you have bladder outlet obstruction or if you are taking other medicines to treat overactive bladder. Tell your doctor right away if you are unable to empty your bladder.
- angioedema. MYRBETRIQ tablets and MYRBETRIQ GRANULES may cause an allergic reaction with swelling of the lips, face, tongue, or throat with or without difficulty breathing. Stop using MYRBETRIQ tablets or MYRBETRIQ GRANULES and go to the nearest hospital emergency room right away.

Adults with Overactive Bladder

The most common side effects of MYRBETRIQ tablets include:

- high blood pressure
- pain or swelling of the nose or throat (nasopharyngitis)
- urinary tract infection
- headache

The most common side effects of MYRBETRIQ tablets, when used with solifenacin succinate, include:

- dry mouth
- urinary tract infection
- constipation
- fast heartbeat

Children with Neurogenic Detrusor Overactivity

The most common side effects of MYRBETRIQ tablets and MYRBETRIQ GRANULES include:

- urinary tract infection
- pain or swelling of the nose or throat (nasopharyngitis)
- constipation
- headache

Tell your doctor if you have any side effect that bothers you, does not go away, or if you have swelling of the face, lips, tongue or throat, hives, skin rash or itching while taking MYRBETRIQ tablets or MYRBETRIQ GRANULES.

These are not all the possible side effects of MYRBETRIQ tablets and MYRBETRIQ GRANULES. For more information, ask your doctor or pharmacist.

Call your doctor for medical advice about side effects. You may report side effects to FDA at 1-800-FDA-1088.

How should I store MYRBETRIQ tablets or MYRBETRIQ GRANULES?

- Store MYRBETRIQ tablets at room temperature between 68°F to 77°F (20°C to 25°C). Keep the bottle closed. Throw away (discard) medicine that is out of date or no longer needed.
- Store MYRBETRIQ GRANULES at room temperature between 68°F to 77°F (20°C to 25°C). Use MYRBETRIQ GRANULES within 28 days (4 weeks) after the date the pharmacist prepares the suspension. The pharmacist will write the expiration date on the bottle. Throw away (discard) any unused medicine after the expiration date.

Keep MYRBETRIQ tablets, MYRBETRIQ GRANULES, and all medicines out of the reach of children.

General information about the safe and effective use of MYRBETRIQ tablets and MYRBETRIQ GRANULES.

Medicines are sometimes prescribed for purposes other than those listed in a Patient Information leaflet. Do not use MYRBETRIQ tablets or MYRBETRIQ GRANULES for a condition for which it was not prescribed. Do not give MYRBETRIQ tablets or MYRBETRIQ GRANULES to other people, even if they have the same symptoms you have. It may harm them.

This leaflet summarizes the most important information about MYRBETRIQ tablets and MYRBETRIQ GRANULES. If you would like more information, talk with your doctor. You can ask your doctor or pharmacist for information about MYRBETRIQ tablets or MYRBETRIQ GRANULES that is written for health professionals.

What are the ingredients in MYRBETRIQ tablets?

Active ingredient: mirabegron

Inactive ingredients: butylated hydroxytoluene, hydroxypropyl cellulose, hypromellose, magnesium stearate, polyethylene glycol, polyethylene oxide, red ferric oxide (25 mg MYRBETRIQ tablet only), and yellow ferric oxide.

What are the ingredients in MYRBETRIQ GRANULES?

Active ingredient: mirabegron

Inactive ingredients: acesulfame potassium, diluted hydrochloric acid, ethylparaben, hypromellose, magnesium stearate, mannitol, methylparaben, silicon dioxide, simethicone, sodium polystyrene sulfonate, and xanthan gum.

Marketed and Distributed by:

Astellas Pharma US, Inc.

Northbrook, IL 60062

MYRBETRIQ and VESIcare are registered trademarks of Astellas Pharma Inc.

All other trademarks are the property of their respective owners.

© 2012 – 2021 Astellas Pharma US, Inc.

For more information, go to www.Myrbetriq.com or call 1-800-727-7003.

This Patient Information has been approved by the U.S. Food and Drug Administration. Revised: 4/2021

PACKAGE/LABEL PRINCIPAL DISPLAY PANEL – 25 mg

NDC 0469-2601-30

Myrbetriq®
(mirabegron extended-release tablets)
25 mg

Once-Daily

Swallow tablet whole.
Do not cut, crush,
or chew tablet.

30 tablets

Rx Only

PACKAGE/LABEL PRINCIPAL DISPLAY PANEL – 50 mg

NDC 0469-2602-30

Myrbetriq®
(mirabegron extended-release tablets)
50 mg

Once-Daily

Swallow tablet whole.
Do not cut, crush,
or chew tablet.

30 tablets

Rx Only

PACKAGE/LABEL PRINCIPAL DISPLAY PANEL – 8 mg/mL

NDC 0469-5020-99

Myrbetriq®
Granules
(mirabegron for extended-release oral suspension)
8 mg/ml

PHARMACIST: Reconstitute product prior to dispensing and dispense with dosing device.
Discard after ____/ ____/ ____

Shake vigorously for 1 minute before each use.

Rx only

100 mL